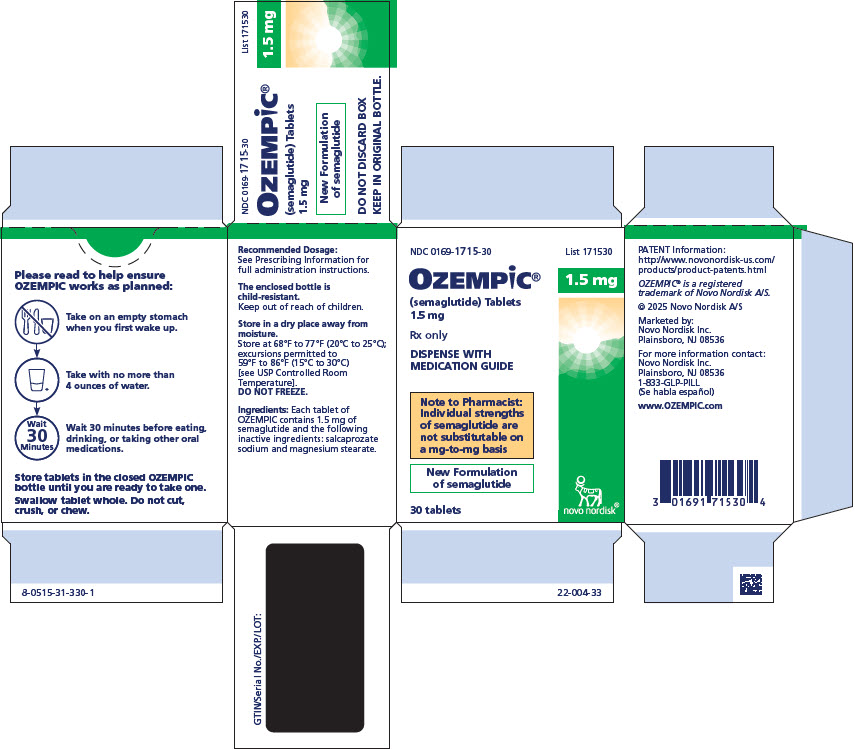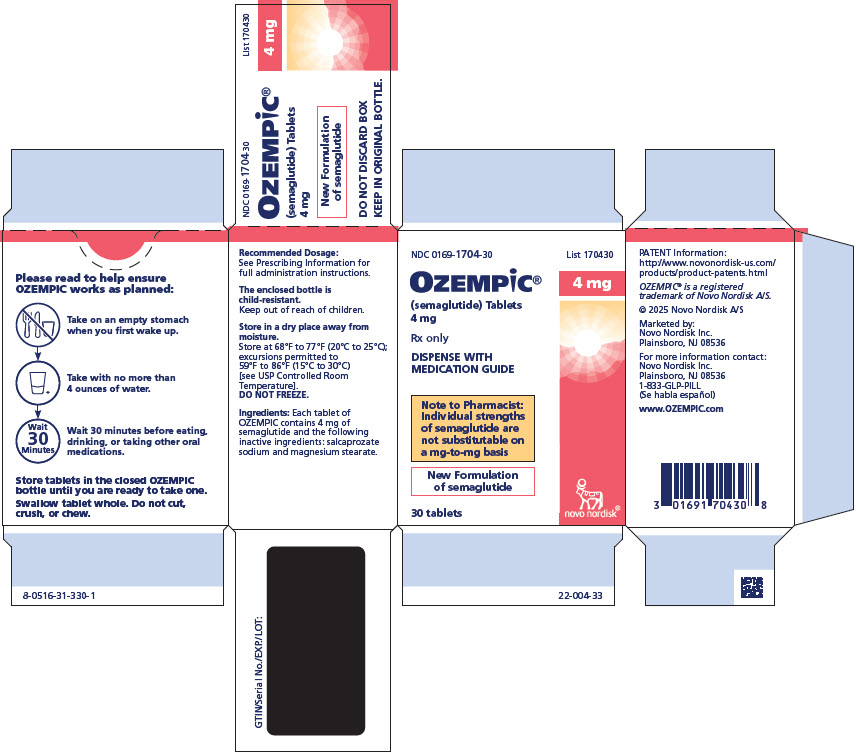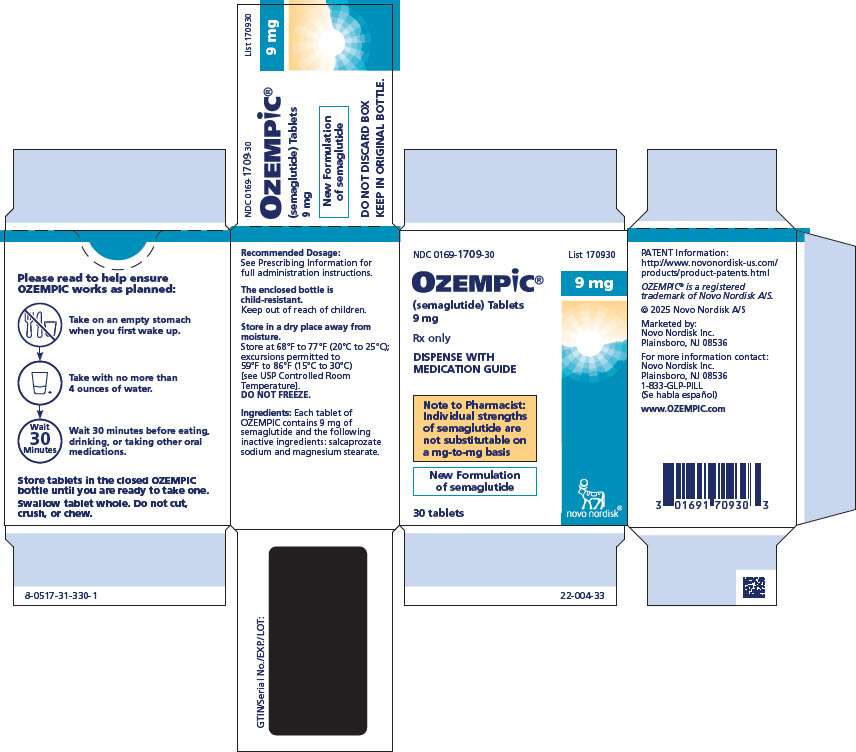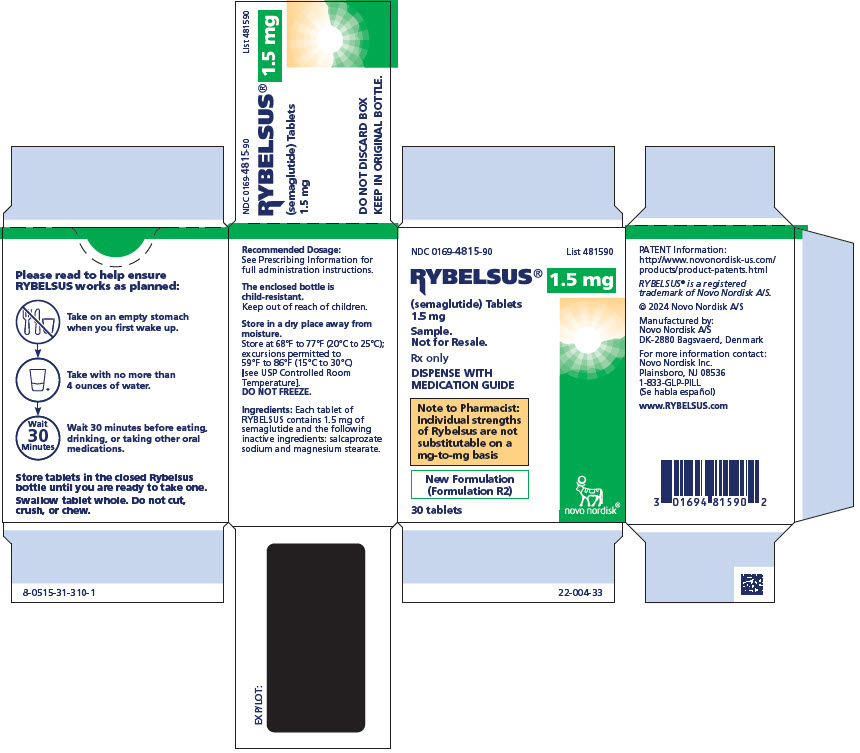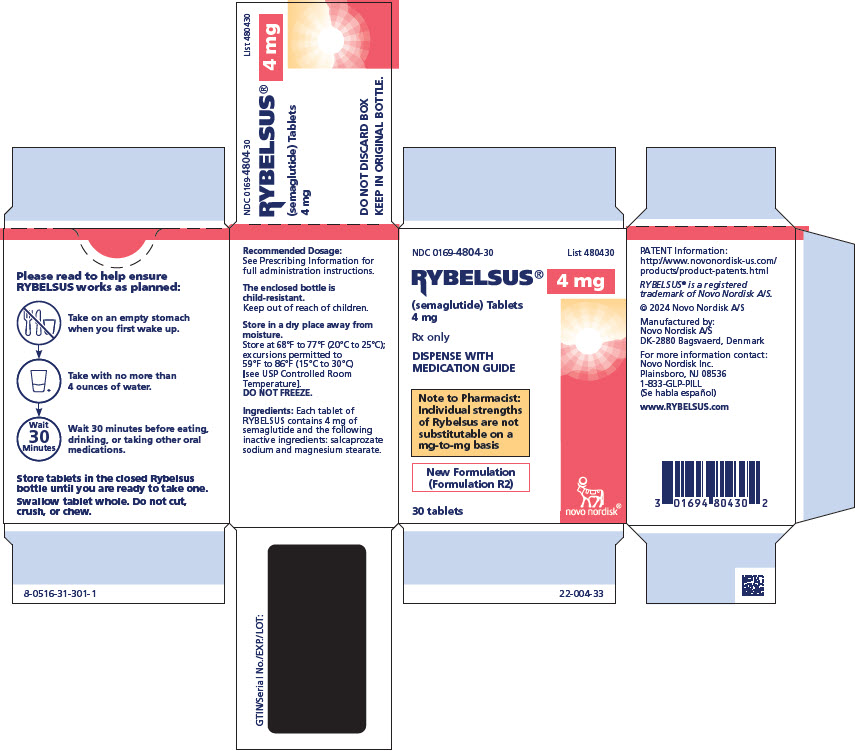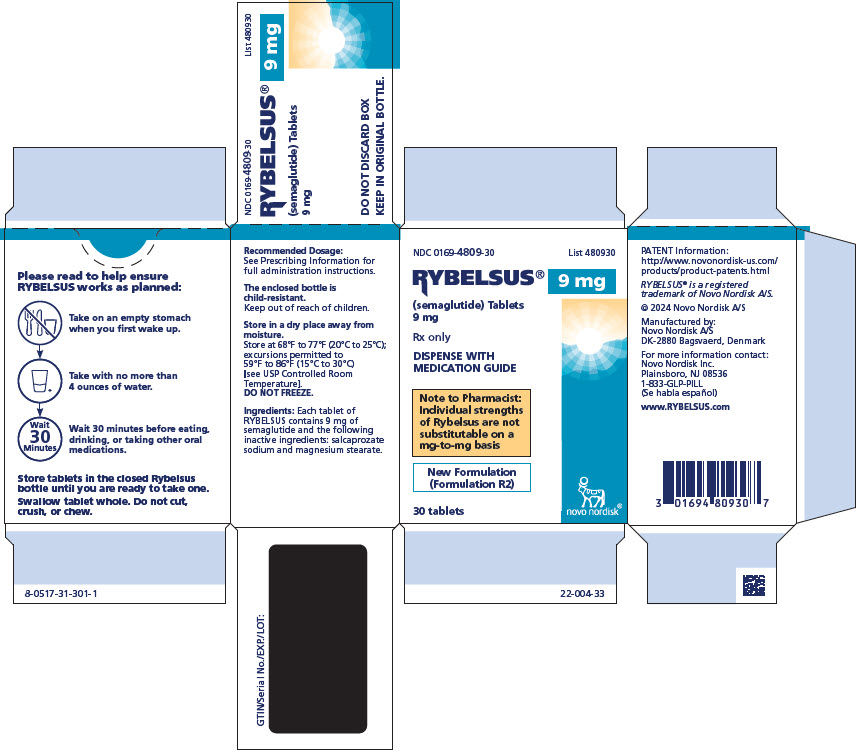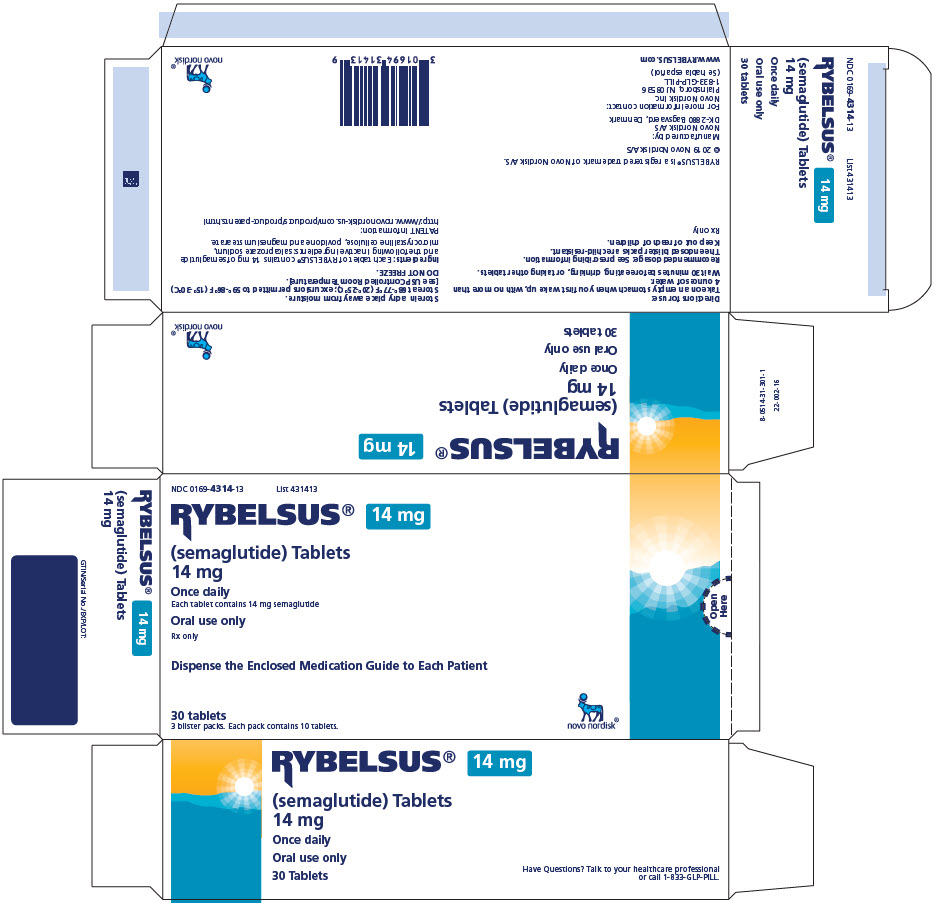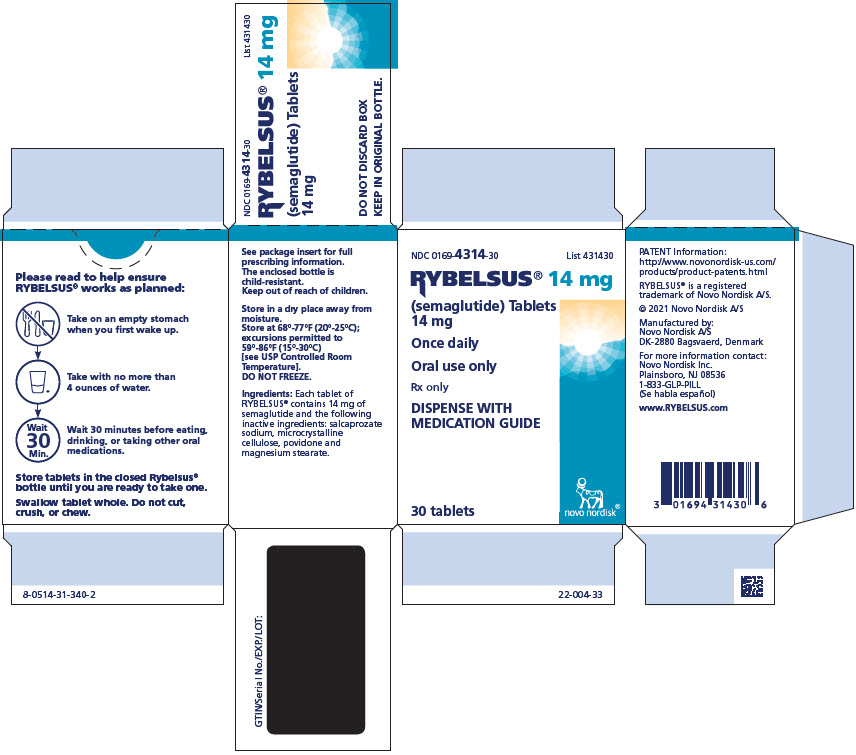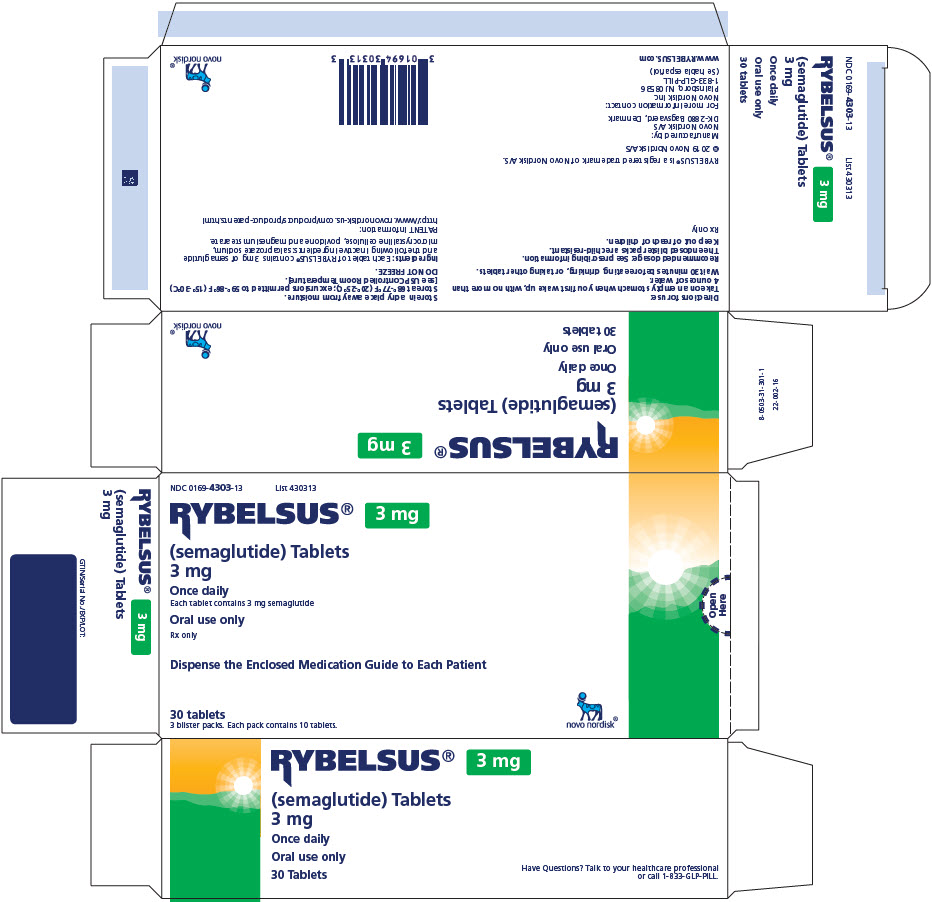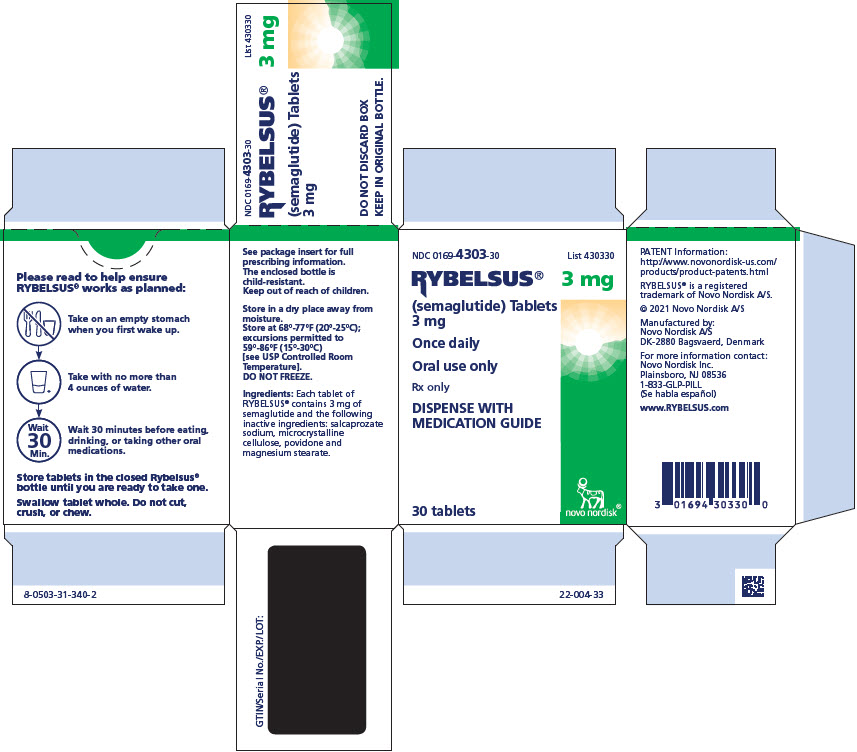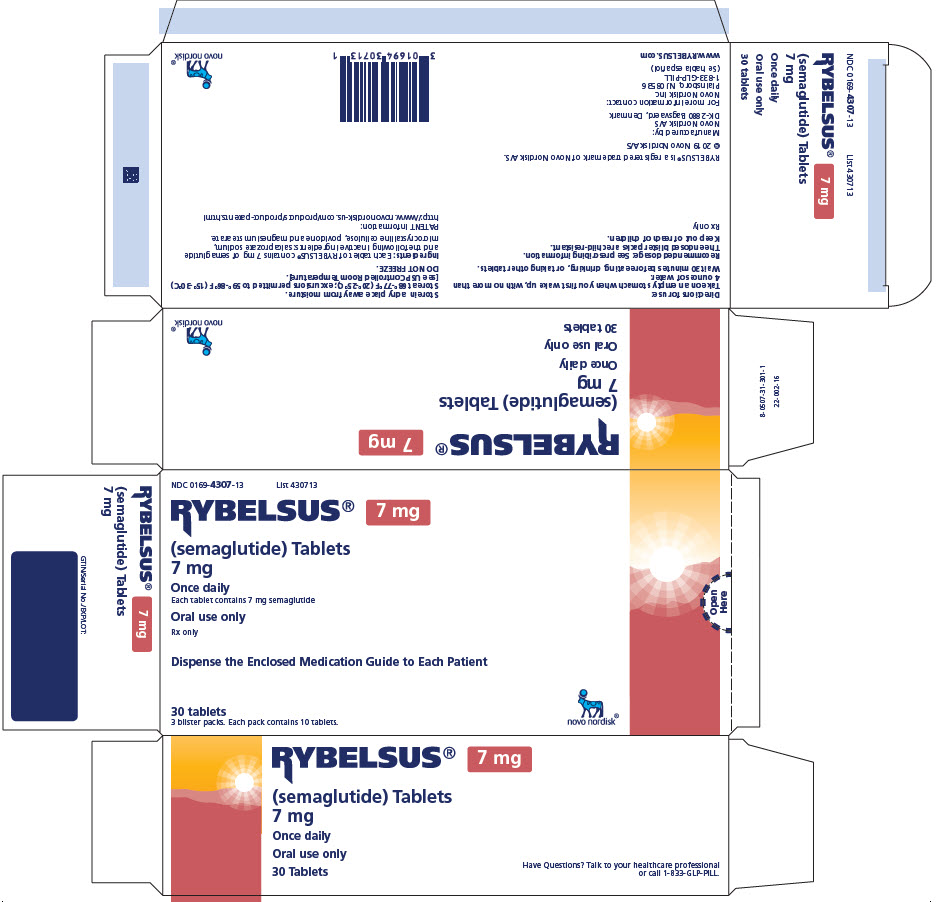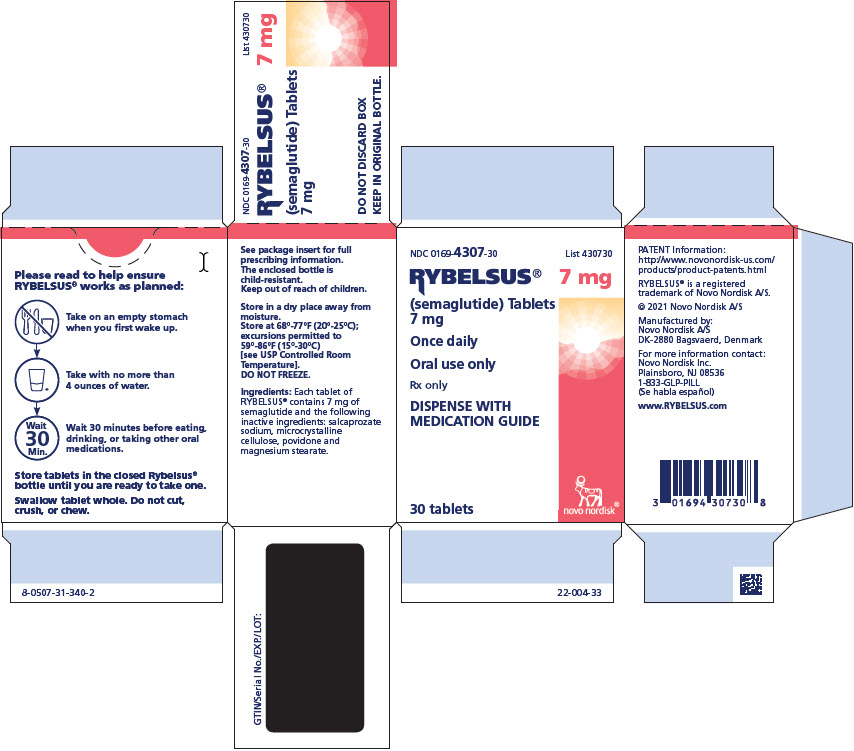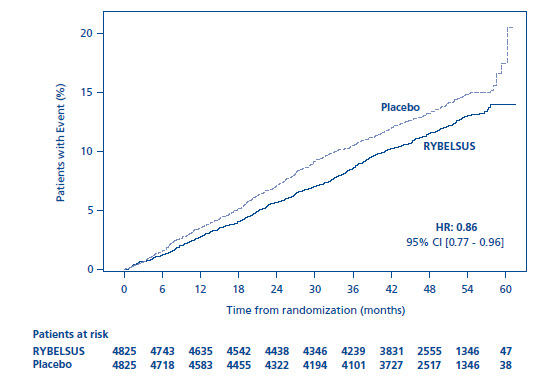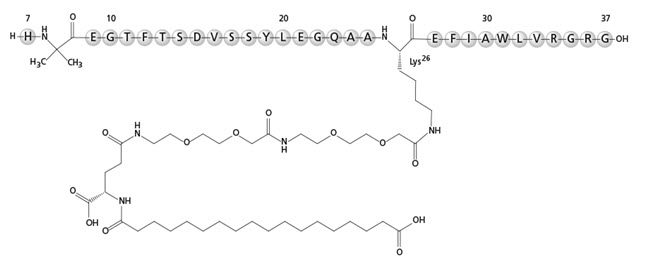 DRUG LABEL: OZEMPIC
NDC: 0169-1715 | Form: TABLET
Manufacturer: Novo Nordisk
Category: prescription | Type: HUMAN PRESCRIPTION DRUG LABEL
Date: 20260130

ACTIVE INGREDIENTS: SEMAGLUTIDE 1.5 mg/1 1
INACTIVE INGREDIENTS: SALCAPROZATE SODIUM; MAGNESIUM STEARATE

HIGHLIGHTS OF PRESCRIBING INFORMATION

These highlights do not include all the information needed to use RYBELSUS® and OZEMPIC® tablets safely and effectively. See full prescribing information for RYBELSUS and OZEMPIC tablets.
RYBELSUS (semaglutide) tablets, for oral use
OZEMPIC (semaglutide) tablets, for oral use
Initial U.S. Approval: 2017

RECENT MAJOR CHANGES

Indications and Usage (1) ………………………………….……..10/2025

Dosage and Administration (2)…………………………..………..12/2025

Warnings and Precautions

Acute Pancreatitis (5.2)……………………………………..…10/2025
Acute Kidney Injury Due to Volume Depletion (5.5) ………..10/2025
Severe Gastrointestinal Adverse Reactions (5.6) ….………….10/2025
Acute Gallbladder Disease (5.8)…………….………..……….10/2025

WARNING: RISK OF THYROID C-CELL TUMORS

See full prescribing information for complete boxed warning.

- In rodents, semaglutide causes thyroid C-cell tumors. It is unknown whether RYBELSUS and OZEMPIC tablets cause thyroid C-cell tumors, including medullary thyroid carcinoma (MTC), in humans as the human relevance of semaglutide-induced rodent thyroid C-cell tumors has not been determined (5.1, 13.1).
- RYBELSUS and OZEMPIC tablets are contraindicated in patients with a personal or family history of MTC or in patients with Multiple Endocrine Neoplasia syndrome type 2 (MEN 2). Counsel patients regarding the potential risk of MTC and symptoms of thyroid tumors (4, 5.1).

1 INDICATIONS AND USAGE

RYBELSUS and OZEMPIC tablets are glucagon-like peptide-1 (GLP-1) receptor agonists indicated:

- as an adjunct to diet and exercise to improve glycemic control in adults with type 2 diabetes mellitus. (1)
- to reduce the risk of major adverse cardiovascular events (cardiovascular death, non-fatal myocardial infarction, or non-fatal stroke) in adults with type 2 diabetes mellitus who are at high risk for these events. (1)

2 DOSAGE AND ADMINISTRATION

- RYBELSUS and OZEMPIC tablets are not substitutable on a mg-to-mg basis.
- Take RYBELSUS or OZEMPIC tablets orally once daily on an empty stomach in the morning with water (up to 4 ounces of water); do not take with other liquids besides water. (2.1)
- Swallow tablets whole. Do not split, crush, chew or dissolve in any solution. (2.1)
- After taking RYBELSUS or OZEMPIC tablets, wait at least 30 minutes before eating food, drinking beverages or taking other oral medications. (2.1)
- See the Full Prescribing Information for instructions on switching between RYBELSUS and OZEMPIC tablets (2.3) and from OZEMPIC injections to RYBELSUS or OZEMPIC tablets. (2.4)

Recommended Starting, Escalation and Maintenance Dosage of RYBELSUS and OZEMPIC Tablets (2.2)

RYBELSUS (2.2)

- Day 1 to 30: Recommended starting dosage is 3 mg orally once daily for 30 days (this dosage is not effective for glycemic control)
- Days 31 to 60: Increase the dosage to 7 mg orally once daily.
- On Day 61 or thereafter, if: (2.2)
- No additional glycemic control is needed, maintain the dosage at 7 mg orally once daily.
- Additional glycemic control is needed, increase the dosage to 14 mg orally once daily.

OZEMPIC Tablets (2.2)

- Day 1 to 30: Recommended starting dosage is 1.5 mg orally once daily for 30 days (this dosage is not effective for glycemic control).
- Days 31 to 60: Increase the dosage to 4 mg orally once daily.
- On Day 61 or thereafter, if: (2.2)
- No additional glycemic control is needed, maintain the dosage at 4 mg orally once daily.
- Additional glycemic control is needed, increase the dosage to 9 mg orally once daily.

3 DOSAGE FORMS AND STRENGTHS

- RYBELSUS tablets: 3 mg, 7 mg and 14 mg (3)
- OZEMPIC tablets: 1.5 mg, 4 mg and 9 mg (3)

4 CONTRAINDICATIONS

- Personal or family history of MTC or in patients with MEN 2 syndrome type 2 (4)
- Prior serious hypersensitivity reaction to semaglutide or any of the excipients in OZEMPIC (4)

5 WARNINGS AND PRECAUTIONS

- Acute Pancreatitis: Has been observed in patients treated with GLP-1 receptor agonists, including RYBELSUS or OZEMPIC tablets. Discontinue if pancreatitis is suspected. (5.2)
- Diabetic Retinopathy Complications: Has been reported in a cardiovascular outcomes trial with semaglutide injection. Patients with a history of diabetic retinopathy should be monitored. (5.3)
- Hypoglycemia with Concomitant Use of Insulin Secretagogues or Insulin: May increase the risk of hypoglycemia, including severe hypoglycemia. Reducing the dosage of insulin secretagogue or insulin may be necessary. (5.4)
- Acute Kidney Injury Due to Volume Depletion: Monitor renal function in patients reporting adverse reactions that could lead to volume depletion. (5.5)
- Severe Gastrointestinal Adverse Reactions: Use of RYBELSUS or OZEMPIC tablets has been associated with gastrointestinal adverse reactions, sometimes severe. RYBELSUS and OZEMPIC tablets are not recommended in patients with severe gastroparesis. (5.6)
- Hypersensitivity Reactions: Serious hypersensitivity reactions (e.g., anaphylaxis and angioedema) have been reported. Discontinue RYBELSUS or OZEMPIC tablets if hypersensitivity reactions occur and monitor until signs and symptoms resolve. (5.7)
- Acute Gallbladder Disease: If cholelithiasis or cholecystitis are suspected, gallbladder studies are indicated. (5.8)
- Pulmonary Aspiration During General Anesthesia or Deep Sedation: Has been reported in patients receiving GLP-1 receptor agonists undergoing elective surgeries or procedures. Instruct patients to inform healthcare providers of any planned surgeries or procedures. (5.9)

6 ADVERSE REACTIONS

Most common adverse reactions (incidence ≥5%) are nausea, abdominal pain, diarrhea, decreased appetite, vomiting and constipation. (6.1)

To report SUSPECTED ADVERSE REACTIONS, contact Novo Nordisk Inc., at 1-833-457-7455 or FDA at 1-800-FDA-1088 or www.fda.gov/medwatch.

7 DRUG INTERACTIONS

Other Oral Drugs: RYBELSUS and OZEMPIC tablets delay gastric emptying. Consider increased clinical or laboratory monitoring when co-administered with other oral medications that have a narrow therapeutic index or that require clinical monitoring. (7.2)

8 USE IN SPECIFIC POPULATIONS

- Pregnancy: See Pregnancy subsection. (8.1)
- Lactation: Breastfeeding not recommended. (8.2)
- Females and Males of Reproductive Potential: Discontinue RYBELSUS or OZEMPIC tablets in women at least 2 months before a planned pregnancy due to the long washout period for semaglutide. (8.3)

FULL PRESCRIBING INFORMATION

WARNING: RISK OF THYROID C-CELL TUMORS

- In rodents, semaglutide causes dose-dependent and treatment-duration-dependent thyroid C-cell tumors at clinically relevant exposures. It is unknown whether RYBELSUS and OZEMPIC tablets cause thyroid C-cell tumors, including medullary thyroid carcinoma (MTC), in humans as human relevance of semaglutide-induced rodent thyroid C-cell tumors has not been determined [see Warnings and Precautions (5.1), Nonclinical Toxicology (13.1)].
- RYBELSUS and OZEMPIC tablets are contraindicated in patients with a personal or family history of MTC or in patients with Multiple Endocrine Neoplasia syndrome type 2 (MEN 2) [see Contraindications (4)]. Counsel patients regarding the potential risk for MTC with the use of RYBELSUS or OZEMPIC tablets and inform them of symptoms of thyroid tumors (e.g., a mass in the neck, dysphagia, dyspnea, persistent hoarseness). Routine monitoring of serum calcitonin or using thyroid ultrasound is of uncertain value for early detection of MTC in patients treated with RYBELSUS or OZEMPIC tablets [see Contraindications (4), Warnings and Precautions (5.1)].

1 INDICATIONS AND USAGE

RYBELSUS and OZEMPIC tablets are indicated:

- as an adjunct to diet and exercise to improve glycemic control in adults with type 2 diabetes mellitus.
- to reduce the risk of major adverse cardiovascular (CV) events (CV death, non-fatal myocardial infarction or non-fatal stroke) in adults with type 2 diabetes mellitus who are at high risk for these events.

2 DOSAGE AND ADMINISTRATION

2.1 Important Administration Instructions

- RYBELSUS and OZEMPIC tablets are not substitutable on a mg-to-mg basis.
- Take one RYBELSUS or OZEMPIC tablet orally once daily on an empty stomach in the morning with water (up to 4 ounces of water). Do not take RYBELSUS or OZEMPIC tablets with other liquids besides water [see Clinical Pharmacology (12.3)].
- Do not take more than one tablet per day.
- Swallow tablets whole. Do not split, crush, chew or dissolve in any solution.
- After taking RYBELSUS or OZEMPIC tablets, wait at least 30 minutes before eating food, drinking beverages or taking other oral medications [see Clinical Pharmacology (12.3)].
- If a dose is missed, skip the missed dose and take the next dose the following day.

2.2 Recommended Starting, Escalation and Maintenance Dosage of RYBELSUS and OZEMPIC Tablets

RYBELSUS: Recommended Dosage

Follow the RYBELSUS starting, escalation, and maintenance dosage described below to reduce the risk of gastrointestinal (GI) adverse reactions [see Warnings and Precautions (5.6), Adverse Reactions (6.1)]:

- Starting Dosage (Initiation Phase) (Days 1 to 30): The recommended starting dosage is 3 mg orally once daily (this dosage is not effective for glycemic control).
- Escalation and Maintenance Dosage (Days 31 and beyond):
- Days 31 to 60: Increase the dosage to 7 mg orally once daily.
- On Day 61 or thereafter, if:
- No additional glycemic control is needed, maintain the dosage at 7 mg orally once daily.
- Additional glycemic control is needed, increase the dosage to 14 mg orally once daily.

OZEMPIC Tablets: Recommended Dosage

Follow the OZEMPIC tablets starting, escalation, and maintenance dosage described below to reduce the risk of GI adverse reactions [see Warnings and Precautions (5.6), Adverse Reactions (6.1)]:

- Starting Dosage (Initiation Phase) (Days 1 through 30): The recommended starting dosage is 1.5 mg orally once daily (this dosage is not effective for glycemic control).
- Escalation and Maintenance Dosage (Days 31 and beyond):
- Days 31 to 60: Increase the dosage to 4 mg orally once daily.
- On Day 61 or thereafter, if:
- No additional glycemic control is needed, maintain the dosage at 4 mg orally once daily.
- Additional glycemic control is needed, increase the dosage to 9 mg orally once daily.

2.3 Switching Between RYBELSUS and OZEMPIC Tablets

- Do not switch between RYBELSUS and OZEMPIC tablets during the initiation phase (Days 1 to 30) [see Dosage and Administration (2.2)].
- After 30 days of RYBELSUS or OZEMPIC tablet treatment (after the initiation phase) [see Dosage and Administration (2.2)], patients may switch between RYBELSUS and OZEMPIC tablet products (see Table 1).
- When switching between RYBELSUS and OZEMPIC tablets, initiate the other semaglutide tablet product the day after discontinuing the previous semaglutide tablet product.

Table 1. Switching Between Escalation or Maintenance Dosage of RYBELSUS and OZEMPIC Tablets

RYBELSUS | OZEMPIC Tablets
7 mg orally once daily | 4 mg orally once daily
14 mg orally once daily | 9 mg orally once daily

2.4 Switching from OZEMPIC Injection to RYBELSUS or OZEMPIC Tablets

Switching from OZEMPIC Injection to RYBELSUS Tablets

- Patients taking the 0.5 mg dose of OZEMPIC injection may switch to RYBELSUS tablets.
- One week after discontinuing 0.5 mg of subcutaneous OZEMPIC injection, start 7 mg or 14 mg of RYBELSUS orally once daily.

Switching from OZEMPIC Injection to OZEMPIC Tablets

- Patients taking the 0.5 mg dose of OZEMPIC injection may switch to OZEMPIC tablets.
- One week after discontinuing 0.5 mg of subcutaneous OZEMPIC injection, start 4 mg or 9 mg of OZEMPIC tablets orally once daily.

3 DOSAGE FORMS AND STRENGTHS

RYBELSUS (semaglutide) tablets are available as:

- 3 mg: white to light yellow, oval shaped debossed with “3” on one side and “novo” on the other side.
- 7 mg: white to light yellow, oval shaped debossed with “7” on one side and “novo” on the other side.
- 14 mg: white to light yellow, oval shaped debossed with “14” on one side and “novo” on the other side.

OZEMPIC (semaglutide) tablets are available as:

- 1.5 mg: white to light yellow, round shaped debossed with “1.5” on one side and “novo” on the other side.
- 4 mg: white to light yellow, round shaped debossed with “4” on one side and “novo” on the other side.
- 9 mg: white to light yellow, round shaped debossed with “9” on one side and “novo” on the other side.

4 CONTRAINDICATIONS

RYBELSUS and OZEMPIC tablets are contraindicated in patients with:

- A personal or family history of medullary thyroid carcinoma (MTC) or in patients with Multiple Endocrine Neoplasia syndrome type 2 (MEN 2) [see Warnings and Precautions (5.1)].
- A prior serious hypersensitivity reaction to semaglutide or to any of the excipients in RYBELSUS or OZEMPIC tablets. Serious hypersensitivity reactions including anaphylaxis and angioedema have been reported with semaglutide tablets [see Warnings and Precautions (5.7)].

5 WARNINGS AND PRECAUTIONS

5.1 Risk of Thyroid C-Cell Tumors

In mice and rats, semaglutide caused a dose-dependent and treatment-duration-dependent increase in the incidence of thyroid C-cell tumors (adenomas and carcinomas) after lifetime exposure at clinically relevant plasma exposures [see Nonclinical Toxicology (13.1)]. It is unknown whether RYBELSUS and OZEMPIC tablets cause thyroid C-cell tumors, including medullary thyroid carcinoma (MTC), in humans as human relevance of semaglutide-induced rodent thyroid C-cell tumors has not been determined.

Cases of MTC in patients treated with liraglutide, another GLP-1 receptor agonist, have been reported in the postmarketing period; the data in these reports are insufficient to establish or exclude a causal relationship between MTC and GLP-1 receptor agonist use in humans.

RYBELSUS and OZEMPIC tablets are contraindicated in patients with a personal or family history of MTC or in patients with MEN 2. Counsel patients regarding the potential risk for MTC with the use of RYBELSUS or OZEMPIC tablets and inform them of symptoms of thyroid tumors (e.g., a mass in the neck, dysphagia, dyspnea, persistent hoarseness).

Routine monitoring of serum calcitonin or using thyroid ultrasound is of uncertain value for early detection of MTC in patients treated with RYBELSUS or OZEMPIC tablets. Such monitoring may increase the risk of unnecessary procedures, due to the low-test specificity for serum calcitonin and a high background incidence of thyroid disease. Significantly elevated serum calcitonin value may indicate MTC and patients with MTC usually have calcitonin values >50 ng/L. If serum calcitonin is measured and found to be elevated, the patient should be further evaluated. Patients with thyroid nodules noted on physical examination or neck imaging should also be further evaluated.

5.2 Acute Pancreatitis

Acute pancreatitis, including fatal and non-fatal hemorrhagic or necrotizing pancreatitis, has been observed in patients treated with GLP-1 receptor agonists, including semaglutide tablets [see Adverse Reactions (6)]. After initiation of RYBELSUS or OZEMPIC tablets, observe patients carefully for signs and symptoms of acute pancreatitis, which may include persistent or severe abdominal pain (sometimes radiating to the back), and which may or may not be accompanied by nausea or vomiting. If pancreatitis is suspected, discontinue RYBELSUS or OZEMPIC tablets and initiate appropriate management.

5.3 Diabetic Retinopathy Complications

In a pooled analysis of glycemic control trials, patients reported diabetic retinopathy related adverse reactions during the trial (4.2% with semaglutide tablets and 3.8% with comparator) [see Adverse Reactions (6.1)].

In a 2-year CV outcomes trial with semaglutide injection involving patients with type 2 diabetes mellitus and high CV risk, diabetic retinopathy complications (which was a 4-component adjudicated endpoint) occurred in patients treated with semaglutide injection (3%) compared to placebo (1.8%). The absolute risk increase for diabetic retinopathy complications was larger among patients with a history of diabetic retinopathy at baseline (semaglutide injection 8.2%, placebo 5.2%) than among patients without a known history of diabetic retinopathy (semaglutide injection 0.7%, placebo 0.4%).

Rapid improvement in glucose control has been associated with a temporary worsening of diabetic retinopathy. The effect of long-term glycemic control with RYBELSUS and OZEMPIC tablets on diabetic retinopathy complications has not been studied. Patients with a history of diabetic retinopathy should be monitored for progression of diabetic retinopathy.

5.4 Hypoglycemia with Concomitant Use of Insulin Secretagogues or Insulin

Patients receiving RYBELSUS or OZEMPIC tablets in combination with an insulin secretagogue (e.g., sulfonylurea) or insulin may have an increased risk of hypoglycemia, including severe hypoglycemia [see Adverse Reactions (6.1), Drug Interactions (7)].

The risk of hypoglycemia may be lowered by a reduction in the dosage of sulfonylurea (or other concomitantly administered insulin secretagogue) or insulin. Inform patients using these concomitant medications of the risk of hypoglycemia and educate them on the signs and symptoms of hypoglycemia.

5.5 Acute Kidney Injury Due to Volume Depletion

There have been postmarketing reports of acute kidney injury in some cases requiring hemodialysis, in patients treated with semaglutide. The majority of the reported events occurred in patients who experienced gastrointestinal reactions leading to dehydration such as nausea, vomiting, or diarrhea [see Adverse Reactions (6)].

Monitor renal function in patients reporting adverse reactions to RYBELSUS or OZEMPIC tablets that could lead to volume depletion, especially during dosage initiation and escalation of RYBELSUS or OZEMPIC tablets.

5.6 Severe Gastrointestinal Adverse Reactions

Use of semaglutide tablets has been associated with gastrointestinal adverse reactions, sometimes severe [see Adverse Reactions (6.1)]. In clinical trials, severe gastrointestinal adverse reactions were reported more frequently among patients who received semaglutide tablets (7 mg 0.6%, 14 mg 2%) than placebo (0.3%). Severe gastrointestinal adverse reactions have also been reported postmarketing with GLP-1 receptor agonists.

RYBELSUS and OZEMPIC tablets are not recommended in patients with severe gastroparesis.

5.7 Hypersensitivity Reactions

Serious hypersensitivity reactions (e.g., anaphylaxis, angioedema) have been reported in patients treated with semaglutide tablets. If hypersensitivity reactions occur, discontinue use of RYBELSUS or OZEMPIC tablets; treat promptly per standard of care and monitor until signs and symptoms resolve. RYBELSUS and OZEMPIC tablets are contraindicated in patients with a prior serious hypersensitivity reaction to semaglutide or to any of the excipients in RYBELSUS or OZEMPIC tablets [see Adverse Reactions (6.2)].

Anaphylaxis and angioedema have been reported with GLP-1 receptor agonists. Use caution in a patient with a history of angioedema or anaphylaxis with another GLP-1 receptor agonist because it is unknown whether such patients will be predisposed to anaphylaxis with RYBELSUS or OZEMPIC tablets.

5.8 Acute Gallbladder Disease

Acute events of gallbladder disease such as cholelithiasis or cholecystitis have been reported in GLP-1 receptor agonist trials and postmarketing. In placebo-controlled trials to improve glycemic control, cholelithiasis was reported in 1% of patients treated with semaglutide tablets (7 mg once daily). In a 4-year CV outcomes trial (Trial 7), cholelithiasis was reported in 1.1% of patients treated with semaglutide tablets (14 mg once daily) and in 0.9% of placebo-treated patients. In Trial 7, cholecystitis was reported in 1.1% of patients treated with semaglutide tablets (14 mg once daily) and in 0.7% of placebo-treated patients [see Adverse Reactions (6.1)]. If cholelithiasis or cholecystitis is suspected, gallbladder studies and appropriate clinical follow-up are indicated [see Adverse Reactions (6.2)].

5.9 Pulmonary Aspiration During General Anesthesia or Deep Sedation

RYBELSUS and OZEMPIC tablets delay gastric emptying [see Clinical Pharmacology (12.2)]. There have been rare postmarketing reports of pulmonary aspiration in patients receiving GLP-1 receptor agonists undergoing elective surgeries or procedures requiring general anesthesia or deep sedation who had residual gastric contents despite reported adherence to preoperative fasting recommendations.

Available data are insufficient to inform recommendations to mitigate the risk of pulmonary aspiration during general anesthesia or deep sedation in patients taking RYBELSUS or OZEMPIC tablets, including whether modifying preoperative fasting recommendations or temporarily discontinuing RYBELSUS or OZEMPIC tablets could reduce the incidence of retained gastric contents. Instruct patients to inform healthcare providers prior to any planned surgeries or procedures if they are taking RYBELSUS or OZEMPIC tablets.

6 ADVERSE REACTIONS

The following serious adverse reactions are described below or elsewhere in the prescribing information:

- Risk of Thyroid C-cell Tumors [see Warnings and Precautions (5.1)]
- Acute Pancreatitis [see Warnings and Precautions (5.2)]
- Diabetic Retinopathy Complications [see Warnings and Precautions (5.3)]
- Hypoglycemia with Concomitant Use of Insulin Secretagogues or Insulin [see Warnings and Precautions (5.4)]
- Acute Kidney Injury Due to Volume Depletion [see Warnings and Precautions (5.5)]
- Severe Gastrointestinal Adverse Reactions [see Warnings and Precautions (5.6)]
- Hypersensitivity Reactions [see Warnings and Precautions (5.7)]
- Acute Gallbladder Disease [see Warnings and Precautions (5.8)]
- Pulmonary Aspiration During General Anesthesia or Deep Sedation [see Warnings and Precautions (5.9)]

6.1 Clinical Trials Experience

Because clinical trials are conducted under widely varying conditions, adverse reaction rates observed in the clinical trials of a drug cannot be directly compared to rates in the clinical trials of another drug and may not reflect the rates observed in practice.

The safety of OZEMPIC tablets (1.5 mg, 4 mg and 9 mg strengths) [see Dosage and Administration (2.2)] and RYBELSUS (3 mg, 7, mg and 14 mg strengths) [see Dosage and Administration (2.2)] has been established as an adjunct to diet and exercise to improve glycemic control in adults with type 2 diabetes mellitus based on adequate and well-controlled studies of RYBELSUS in adult patients with type 2 diabetes mellitus [see Clinical Pharmacology (12.3), Clinical Studies (14)]. Below is a display of the safety results of the adequate and well-controlled studies of RYBELSUS (referred to below as semaglutide tablets) in adult patients with type 2 diabetes mellitus.

Pool of Placebo-Controlled Trials

The data in Table 2 are derived from 2 placebo-controlled trials in adult patients with type 2 diabetes mellitus [see Clinical Studies (14)]. These data reflect exposure of 1,071 patients to semaglutide tablets (3 mg, 7, mg or 14 mg orally once daily) with a mean duration of exposure of 41.8 weeks. The mean age of patients was 58 years, 3.9% were 75 years or older and 52% were male. In these trials, 63% were White, 6% were Black or African American and 27% were Asian; 19% identified as Hispanic or Latino ethnicity. At baseline, patients had type 2 mellitus diabetes for an average of 9.4 years and had a mean HbA1c of 8.1%. At baseline, 20.1% of the population reported retinopathy. Baseline estimated renal function was normal (eGFR ≥90 mL/min/1.73m^2) in 66.2%, mildly impaired (eGFR 60 to 90 mL/min/1.73m^2) in 32.4% and moderately impaired (eGFR 30 to 60 mL/min/1.73m^2) in 1.4% of patients.

Pool of Placebo- and Active-Controlled Trials

The occurrence of adverse reactions was also evaluated in a larger pool of adult patients with type 2 diabetes mellitus participating in 9 placebo- and active-controlled trials [see Clinical Studies (14)]. In this pool, 4,116 patients with type 2 diabetes mellitus were treated with semaglutide tablets for a mean duration of 59.8 weeks. The mean age of patients was 58 years, 5% were 75 years or older and 55% were male. In these trials, 65% were White, 6% were Black or African American and 24% were Asian; 15% identified as Hispanic or Latino ethnicity. At baseline, patients had type 2 diabetes mellitus for an average of 8.8 years and had a mean HbA1c of 8.2%. At baseline, 16.6% of the population reported retinopathy. Baseline estimated renal function was normal (eGFR ≥90 mL/min/1.73m^2) in 65.9%, mildly impaired (eGFR 60 to 90 mL/min/1.73m^2) in 28.5% and moderately impaired (eGFR 30 to 60 mL/min/1.73m^2) in 5.4% of the patients.

Common Adverse Reactions

Table 2 shows common adverse reactions, excluding hypoglycemia, associated with the use of semaglutide tablets in adult patients with type 2 diabetes mellitus in the pool of placebo-controlled trials. These adverse reactions occurred more commonly on semaglutide tablets than on placebo and occurred in at least 5% of patients treated with semaglutide tablets.

Table 2. Adverse Reactions in Placebo-Controlled Trials Reported in ≥5% of Semaglutide Tablets-Treated Patients with Type 2 Diabetes Mellitus

Adverse Reaction | Placebo; (N=362); % | Semaglutide Tablets; 7 mg; (N=356); % | Semaglutide Tablets; 14 mg; (N=356); %
Nausea | 6 | 11 | 20
Abdominal Pain | 4 | 10 | 11
Diarrhea | 4 | 9 | 10
Decreased appetite | 1 | 6 | 9
Vomiting | 3 | 6 | 8
Constipation | 2 | 6 | 5

In the pool of placebo- and active-controlled trials, the types and frequency of common adverse reactions, excluding hypoglycemia, were similar to those listed in Table 2.

In a 4-year CV outcomes trial (Trial 7), 4,825 patients were randomized to semaglutide tablets for a median follow-up of 49.6 months and 4,825 patients were randomized to placebo for a median follow-up of 49.4 months [see Clinical Studies (14.4)]. Safety data collection was limited to serious adverse events (including death), adverse events leading to discontinuation, and adverse events of special interest. Study drug was permanently discontinued due to an adverse event in 15.5% of semaglutide tablets-treated patients and 11.6% of placebo-treated patients.

Additional information from this trial is included in subsequent sections below, when relevant.

Gastrointestinal Adverse Reactions

In the pool of placebo-controlled trials, gastrointestinal adverse reactions occurred more frequently among patients who received semaglutide tablets than placebo: semaglutide tablets 14 mg once daily (41%), semaglutide tablets 7 mg once daily (32%) and placebo (21%), including severe reactions (semaglutide tablets 14 mg 2.0%, semaglutide tablets 7 mg 0.6%, placebo 0.3%). The majority of reports of nausea, vomiting and/or diarrhea occurred during dose escalation. A greater percentage of patients who received semaglutide tablets 14 mg once daily (8%) and semaglutide tablets 7 mg once daily (4%) discontinued treatment due to gastrointestinal adverse reactions than patients who received placebo (1%).

In addition to the reactions in Table 2, the following gastrointestinal adverse reactions with a frequency of <5% occurred in semaglutide tablets -treated patients (frequencies listed, respectively, as 14 mg once daily, 7 mg once daily and placebo): abdominal distension (3%, 2% and 1%), dyspepsia (0.6%, 3%, 0.6%), eructation (2%, 0.6%, 0%,), flatulence (1%, 2%, 0%), gastroesophageal reflux disease (2%, 2%, 0.3%) and gastritis (2%, 2%, 0.8%).

Other Adverse Reactions

Pancreatitis: In the pool of placebo- and active-controlled trials with semaglutide tablets, pancreatitis was reported as a serious adverse event in 6 semaglutide tablets -treated patients (0.1 events per 100 patient years) versus 1 in comparator-treated patients (<0.1 events per 100 patient years).

Diabetic Retinopathy Complications: In the pool of placebo- and active-controlled trials with semaglutide tablets, patients reported diabetic retinopathy related adverse reactions during the trial (4.2% with semaglutide tablets and 3.8% with comparator).

Hypoglycemia: Table 3 summarizes the incidence of hypoglycemia by various definitions in the placebo-controlled trials.

Table 3. Hypoglycemia Adverse Reactions in Placebo-Controlled Trials in Patients with Type 2 Diabetes Mellitus

 | Placebo | Semaglutide Tablets; 7 mg | Semaglutide Tablets; 14 mg
Monotherapy
(26 weeks) | N=178 | N=175 | N=175
Severe* | 0% | 1% | 0%
Plasma glucose <54 mg/dL | 1% | 0% | 0%
Add-on to metformin and/or sulfonylurea, basal insulin alone or metformin in combination with basal insulin in patients with moderate renal impairment
(26 weeks) | N=161 | - | N=163
Severe* | 0% | - | 0%
Plasma glucose <54 mg/dL | 3% | - | 6%
Add-on to insulin with or without metformin
(52 weeks) | N=184 | N=181 | N=181
Severe* | 1% | 0% | 1%
Plasma glucose <54 mg/dL | 32% | 26% | 30%

* “Severe” hypoglycemia adverse reactions are episodes requiring the assistance of another person.

Hypoglycemia was more frequent when semaglutide tablets were used in combination with insulin secretagogues (e.g., sulfonylureas) or insulin.

Increases in Amylase and Lipase: In placebo-controlled trials, patients exposed to semaglutide tablets 7 mg and 14 mg tablets had a mean increase from baseline in amylase of 10% and 13%, respectively and lipase of 30% and 34%, respectively. These changes were not observed in placebo-treated patients.

Cholelithiasis: In placebo-controlled trials to improve glycemic control, cholelithiasis was reported in 1% of patients treated with semaglutide tablets 7 mg.

In a 4-year CV outcomes trial (Trial 7), cholelithiasis was reported in 1.1% of patients treated with semaglutide 14 mg tablets and in 0.9% of placebo-treated patients. In Trial 7, cholecystitis was reported in 1.1% of patients treated with semaglutide14 mg tablets and in 0.7% of placebo-treated patients.

Increases in Heart Rate: In placebo-controlled trials, semaglutide tablets 7 mg and 14 mg tablets resulted in a mean increase in heart rate of 1 to 3 beats per minute. There was no change in heart rate in placebo-treated patients.

6.2 Postmarketing Experience

The following adverse reactions have been reported during post-approval use of semaglutide, the active ingredient in RYBELSUS and OZEMPIC tablets. Because these reactions are reported voluntarily from a population of uncertain size, it is not always possible to reliably estimate their frequency or establish a causal relationship to drug exposure.

- Gastrointestinal: acute pancreatitis and necrotizing pancreatitis, sometimes resulting in death; ileus, intestinal obstruction, severe constipation including fecal impaction
- Hypersensitivity: anaphylaxis, angioedema, rash, urticaria
- Hepatobiliary: cholecystitis, cholelithiasis requiring cholecystectomy
- Nervous system disorders: dizziness, dysesthesia, dysgeusia, headache
- Pulmonary: Pulmonary aspiration has occurred in patients receiving GLP-1 receptor agonists undergoing elective surgeries or procedures requiring general anesthesia or deep sedation
- Renal: acute kidney injury
- Skin and Subcutaneous Tissue: alopecia

7 DRUG INTERACTIONS

7.1 Concomitant Use with an Insulin Secretagogue (e.g., Sulfonylurea) or with Insulin

Semaglutide stimulates insulin release in the presence of elevated blood glucose concentrations. Patients receiving RYBELSUS or OZEMPIC tablets in combination with an insulin secretagogue (e.g., sulfonylurea) or insulin may have an increased risk of hypoglycemia, including severe hypoglycemia.

When initiating RYBELSUS or OZEMPIC tablets, consider reducing the dosage of concomitantly administered insulin secretagogue (such as sulfonylureas) or insulin to reduce the risk of hypoglycemia [see Warnings and Precautions (5.4), Adverse Reactions (6.1)].

7.2 Other Oral Drugs

Semaglutide cause a delay of gastric emptying and thereby has the potential to impact the absorption of other oral drugs. Levothyroxine exposure was increased 33% (90% CI: 1.25 to 1.42) when administered with semaglutide tablets in a drug interaction study [see Clinical Pharmacology (12.3)].

When using RYBELSUS or OZEMPIC tablets concomitantly with other oral drugs that have a narrow therapeutic index or that require clinical monitoring, consider increased clinical or laboratory monitoring [see Dosage and Administration (2)].

8 USE IN SPECIFIC POPULATIONS

8.1 Pregnancy

Risk Summary

Available data with semaglutide use in pregnant women are insufficient to evaluate for a drug-associated risk of major birth defects, miscarriage or other adverse maternal or fetal outcomes. There are clinical considerations regarding the risks of poorly controlled diabetes in pregnancy (see Clinical Considerations). Based on animal reproduction studies, there may be potential risks to the fetus from exposure to semaglutide during pregnancy. RYBELSUS or OZEMPIC tablets should be used during pregnancy only if the potential benefit justifies the potential risk to the fetus.

In pregnant rats administered semaglutide during organogenesis, embryofetal mortality, structural abnormalities and alterations to growth occurred at maternal exposures below the maximum recommended human dose (MRHD) based on AUC. In rabbits and cynomolgus monkeys administered semaglutide during organogenesis, early pregnancy losses and structural abnormalities were observed at exposure below the MRHD (rabbit) and ≥10-fold the MRHD (monkey). These findings coincided with a marked maternal body weight loss in both animal species (see Data).

The estimated background risk of major birth defects is 6% to 10% in women with pre-gestational diabetes with an HbA1c >7 and has been reported to be as high as 20% to 25% in women with an HbA1c >10. In the U.S. general population, the estimated background risk of major birth defects and miscarriage in clinically recognized pregnancies is 2% to 4% and 15% to 20%, respectively.

Clinical Considerations

Disease Associated Maternal and Fetal Risk: Poorly controlled diabetes during pregnancy increases the maternal risk for diabetic ketoacidosis, preeclampsia, spontaneous abortions, preterm delivery and delivery complications. Poorly controlled diabetes increases the fetal risk for major birth defects, stillbirth and macrosomia related morbidity.

Data

Animal Data: In a combined fertility and embryofetal development study in rats, subcutaneous doses of 0.01, 0.03 and 0.09 mg/kg/day (0.2-, 0.7- and 2.1-fold the MRHD) were administered to males for 4 weeks prior to and throughout mating and to females for 2 weeks prior to mating, and throughout organogenesis to Gestation Day 17. In parental animals, pharmacologically mediated reductions in body weight gain and food consumption were observed at all dose levels. In the offspring, reduced growth and fetuses with visceral (heart blood vessels) and skeletal (cranial bones, vertebra, ribs) abnormalities were observed at the human exposure.

In an embryofetal development study in pregnant rabbits, subcutaneous doses of 0.0010, 0.0025 or 0.0075 mg/kg/day (0.06-, 0.6- and 4.4-fold the MRHD) were administered throughout organogenesis from Gestation Day 6 to 19. Pharmacologically mediated reductions in maternal body weight gain and food consumption were observed at all dose levels. Early pregnancy losses and increased incidences of minor visceral (kidney, liver) and skeletal (sternebra) fetal abnormalities were observed at ≥0.0025 mg/kg/day, at clinically relevant exposures.

In an embryofetal development study in pregnant cynomolgus monkeys, subcutaneous doses of 0.015, 0.075 and 0.15 mg/kg twice weekly (1.9-, 9.9- and 29-fold the MRHD) were administered throughout organogenesis, from Gestation Day 16 to 50. Pharmacologically mediated, marked initial maternal body weight loss and reductions in body weight gain and food consumption coincided with the occurrence of sporadic abnormalities (vertebra, sternebra, ribs) at ≥0.075 mg/kg twice weekly (≥9X human exposure).

In a pre- and postnatal development study in pregnant cynomolgus monkeys, subcutaneous doses of 0.015, 0.075 and 0.15 mg/kg twice weekly (1.3-, 6.4- and 14-fold the MRHD) were administered from Gestation Day 16 to 140. Pharmacologically mediated marked initial maternal body weight loss and reductions in body weight gain and food consumption coincided with an increase in early pregnancy losses and led to delivery of slightly smaller offspring at ≥0.075 mg/kg twice weekly (≥6X human exposure).

Salcaprozate sodium (SNAC), an absorption enhancer in RYBELSUS and OZEMPIC tablets, crosses the placenta and reaches fetal tissues in rats. In a pre- and postnatal development study in pregnant Sprague Dawley rats, SNAC was administered orally at 1,000 mg/kg/day (exposure levels were not measured) on Gestation Day 7 through Lactation Day 20. An increase in gestation length, an increase in the number of stillbirths and a decrease in pup viability were observed.

8.2 Lactation

Risk Summary

A clinical lactation study reported semaglutide concentrations below the lower limit of quantification in human breast milk. However, SNAC and/or its metabolites are present in human milk. Since the activity of enzymes involved in SNAC clearance may be lower in infants compared to adults, higher SNAC plasma levels may occur in neonates and infants. Because of the unknown potential for serious adverse reactions in the breastfed infant due to the possible accumulation of SNAC, and because there are alternative semaglutide products that do not contain SNAC that can be used during lactation, advise patients that breastfeeding is not recommended during treatment with RYBELSUS or OZEMPIC tablets.

8.3 Females and Males of Reproductive Potential

Discontinue RYBELSUS or OZEMPIC tablets in women at least 2 months before a planned pregnancy due to the long washout period for semaglutide [see Use in Specific Populations (8.1)].

8.4 Pediatric Use

The safety and effectiveness of RYBELSUS and OZEMPIC tablets have not been established in pediatric patients.

8.5 Geriatric Use

In the pool of glycemic control trials, 1,229 (30%) patients treated with semaglutide tablets were 65 years of age and over and 199 (5%) patients treated with semaglutide tablets were 75 years of age and over [see Clinical Studies (14)]. In Trial 8, one of the CV outcomes trials, 891 (56%) patients treated with semaglutide tablets were 65 years of age and over and 200 (13%) patients treated with semaglutide tablets were 75 years of age and over.

No overall differences in safety or effectiveness for semaglutide tablets have been observed between patients 65 years of age and older and younger adult patients.

8.6 Renal Impairment

The recommended dosage of RYBELSUS and OZEMPIC tablets in patients with renal impairment is the same as those with normal renal function.

The safety and effectiveness of semaglutide tablets was evaluated in a 26-week clinical study that included 324 patients with moderate renal impairment (eGFR 30 to 59 mL/min/1.73 m^2) [see Clinical Studies (14.1)]. In patients with renal impairment including end-stage renal disease (ESRD), no clinically relevant change in semaglutide pharmacokinetics was observed [see Clinical Pharmacology (12.3)].

8.7 Hepatic Impairment

The recommended dosage in patients with hepatic impairment is the same as those with normal hepatic function.

In a study in subjects with different degrees of hepatic impairment, no clinically relevant change in semaglutide pharmacokinetics was observed [see Clinical Pharmacology (12.3)].

10 OVERDOSAGE

In the event of overdose, appropriate supportive treatment should be initiated according to the patient’s clinical signs and symptoms. Consider contacting the Poison Help line (1-800-222-1222) or a medical toxicologist for additional overdosage management recommendations. A prolonged period of observation and treatment for these symptoms may be necessary, taking into account the long half-life of semaglutide of approximately 1 week.

11 DESCRIPTION

RYBELSUS and OZEMPIC tablets, for oral use, contain semaglutide, a GLP-1 receptor agonist. The peptide backbone is produced by yeast fermentation. The main protraction mechanism of semaglutide is albumin binding, facilitated by modification of position 26 lysine with a hydrophilic spacer and a C18 fatty di-acid. Furthermore, semaglutide is modified in position 8 to provide stabilization against degradation by the enzyme dipeptidyl-peptidase 4 (DPP-4). A minor modification was made in position 34 to ensure the attachment of only one fatty di-acid. The molecular formula is C187H291N45O59 and the molecular weight is 4113.58 g/mol.

Structural formula:

Semaglutide is a white to almost white hygroscopic powder.

RYBELSUS tablets contain 3 mg, 7 mg or 14 mg of semaglutide and the following inactive ingredients: magnesium stearate, microcrystalline cellulose, povidone and salcaprozate sodium (SNAC).

OZEMPIC tablets contain 1.5 mg, 4 mg or 9 mg of semaglutide and the following inactive ingredients: magnesium stearate and SNAC.

12 CLINICAL PHARMACOLOGY

12.1 Mechanism of Action

Semaglutide is a GLP-1 analogue with 94% sequence homology to human GLP-1. Semaglutide acts as a GLP-1 receptor agonist that selectively binds to and activates the GLP-1 receptor, the target for native GLP-1.

GLP-1 is a physiological hormone that has multiple actions on glucose, mediated by the GLP-1 receptors.

The principal mechanism of protraction resulting in the long half-life of semaglutide is albumin binding, which results in decreased renal clearance and protection from metabolic degradation. Furthermore, semaglutide is stabilized against degradation by the DPP-4 enzyme.

Semaglutide reduces blood glucose through a mechanism where it stimulates insulin secretion and lowers glucagon secretion, both in a glucose-dependent manner. Thus, when blood glucose is high, insulin secretion is stimulated and glucagon secretion is inhibited. The mechanism of blood glucose lowering also involves a minor delay in gastric emptying in the early postprandial phase.

12.2 Pharmacodynamics

The pharmacodynamic evaluations described below were in patients with type 2 diabetes mellitus who received once-weekly subcutaneous injections of placebo or semaglutide injection over 12 weeks (semaglutide injection-treated patients were started on lower dosages and then titrated up to 1 mg once weekly). RYBELSUS and OZEMPIC tablets are not approved for subcutaneous use.

Fasting and Postprandial Glucose

Semaglutide reduces fasting and postprandial glucose concentrations. In patients with type 2 diabetes mellitus, treatment with semaglutide injection 1 mg resulted in reductions in glucose in terms of absolute change from baseline and relative reduction compared to placebo of 29 mg/dL (22%) for fasting glucose, 74 mg/dL (36%) for 2-hour postprandial glucose and 30 mg/dL (22%) for mean 24-hour glucose concentration.

Insulin Secretion

Both first- and second-phase insulin secretion are increased in patients with type 2 diabetes mellitus treated with semaglutide compared with placebo.

Glucagon Secretion

Semaglutide lowers the fasting and postprandial glucagon concentrations.

Glucose dependent insulin and glucagon secretion

Semaglutide lowers high blood glucose concentrations by stimulating insulin secretion and lowering glucagon secretion in a glucose-dependent manner.

During induced hypoglycemia, semaglutide did not alter the counter regulatory responses of increased glucagon compared to placebo and did not impair the decrease of C-peptide in patients with type 2 diabetes mellitus.

Gastric emptying

Semaglutide causes a delay of early postprandial gastric emptying, thereby reducing the rate at which glucose appears in the circulation postprandially.

Cardiac Electrophysiology

The effect of subcutaneously administered semaglutide on cardiac repolarization was tested in a thorough QTc trial. At an average exposure level 4-fold higher than that of the maximum recommended dose of semaglutide tablets, semaglutide does not prolong QTc intervals to any clinically relevant extent.

12.3 Pharmacokinetics

Semaglutide estimated mean steady-state concentration was 6.7 nmol/L and 14.6 nmol/L following once daily oral administration of 7 mg and 14 mg of RYBELSUS, respectively, in patients with type 2 diabetes mellitus.

Semaglutide exposures increased in a dose-proportional manner. Steady-state exposure was achieved following 4 to 5 weeks of semaglutide tablets oral administration.

Absorption

RYBELSUS and OZEMPIC tablets are co-formulated with SNAC which facilitates the absorption of semaglutide after oral administration. The absorption of semaglutide predominantly occurs in the stomach.

Semaglutide estimated absolute bioavailability was approximately:

- 0.4% to 1% after oral administration of 3 mg, 7 mg and 14 mg of RYBELSUS.
- 1% to 2% after oral administration of 1.5 mg, 4 mg and 9 mg of OZEMPIC tablets.

Semaglutide maximum concentration was reached approximately 1-hour after oral administration of semaglutide tablets.

Effect of Semaglutide Tablet Formulations: There were no clinically significant differences observed in the mean steady state AUC0-24h,SS and Cmax,SS between the 3 mg, 7 mg and 14 mg doses of RYBELSUS and the 1.5 mg, 4 mg and 9 mg doses of OZEMPIC tablets, respectively, in a clinical study conducted in healthy subjects.

Effect of Volume and Timing of Water Consumption: Single oral doses of semaglutide tablets were administered with 50 mL or 240 mL of water after an 8-hour overnight fast and a continued fast of 4 hours post-dose in healthy subjects. Semaglutide absorption (i.e., area under the curve (AUC) and peak concentrations (Cmax) were higher following dosing with 50 mL water compared to that of 240 mL water.

For 10 days, healthy subjects received semaglutide tablets once daily doses orally with 50 mL or 120 mL of water under fasting conditions with post-dose fasting period of 15, 30, 60 or 120 minutes. In this study, semaglutide absorption (i.e., AUC and Cmax) was higher after a longer post-dose fasting period. There were no clinically significant differences in semaglutide absorption with administration of 50 mL or 120 mL of water.

Distribution

Semaglutide absolute volume of distribution is approximately 8 L in patients with type 2 diabetes. Semaglutide is >99% bound to plasma albumin.

Elimination

Semaglutide elimination half-life is approximately one week with an absolute clearance of approximately 0.04 L/hour in patients with type 2 diabetes. Semaglutide is present in the circulation for about five weeks after the last semaglutide tablet dose.

Metabolism: The primary route of elimination for semaglutide is metabolism following proteolytic cleavage of the peptide backbone and sequential beta-oxidation of the fatty acid side chain.

Excretion: The primary excretion routes of semaglutide-related material are via the urine and feces. Approximately 3% of the absorbed dose is excreted in the urine as intact semaglutide.

Specific Populations

No clinically significant differences in semaglutide pharmacokinetics were observed based on age (≥18 years old), sex, race (White, Asian or Black or African American), ethnicity, body weight (40 to 188 kg), upper GI disease (i.e., chronic gastritis and/or gastroesophageal reflux disease), hepatic impairment (i.e., mild, moderate, severe based on the Child-Pugh system) and renal impairment (i.e., mild, moderate, severe, end staged renal disease).

Drug Interaction Studies

Clinical Studies and Model-Informed Approaches: The delay of gastric emptying with semaglutide may influence the absorption of concomitantly administered oral drugs. Trials were conducted to study the potential effect of semaglutide on the absorption of oral drugs taken with semaglutide administered orally at steady-state exposure.

Levothyroxine: Total thyroxine (i.e., adjusted for endogenous levels) AUC was increased by 33% following administration of a single dose of levothyroxine 600 mcg concomitantly administered with semaglutide tablets. Maximum exposure (Cmax) was unchanged.
Other Drugs: No clinically significant differences in semaglutide pharmacokinetics were observed when used concomitantly with omeprazole. No clinically significant differences in the pharmacokinetics of the following drugs were observed when used concomitantly with semaglutide: lisinopril, S-warfarin, R-warfarin, metformin, digoxin, ethinyl estradiol, levonorgestrel, furosemide or rosuvastatin.

In Vitro Studies: Semaglutide has very low potential to inhibit or induce CYP enzymes, and to inhibit drug transporters.

12.6 Immunogenicity

The observed incidence of anti-drug antibodies is highly dependent on the sensitivity and specificity of the assay. Differences in assay methods preclude meaningful comparisons of the incidence of anti-drug antibodies in the studies described below with the incidence of anti-drug antibodies in other studies, including those of semaglutide or of other semaglutide products.

During the 26- to 78-week treatment periods in 5 clinical trials in adults with type 2 diabetes mellitus [see Clinical Studies (14.2, 14.3)] and 1 clinical trial in Japanese adults with type 2 diabetes mellitus, 14/2,924 (0.5%) of semaglutide tablet-treated patients developed anti-semaglutide antibodies. Of these 14 semaglutide tablet -treated patients, 7 patients (0.2% of the total semaglutide tablet-treated study population) developed antibodies that cross-reacted with native GLP-1. No identified clinically significant effect of anti-semaglutide antibodies on pharmacokinetics of semaglutide tablets was observed. There is insufficient information to characterize the effects of anti-semaglutide antibodies on pharmacodynamics, safety or effectiveness of semaglutide.

13 NONCLINICAL TOXICOLOGY

13.1 Carcinogenesis, Mutagenesis, Impairment of Fertility

In a 2-year carcinogenicity study in CD-1 mice, subcutaneous doses of 0.3, 1 and 3 mg/kg/day [9-, 33- and 113- fold the maximum recommended human dose (MRHD) of semaglutide tablet 14 mg, based on AUC] were administered to the males, and 0.1, 0.3 and 1 mg/kg/day (3-, 9- and 33-fold MRHD) were administered to the females. A statistically significant increase in thyroid C-cell adenomas and a numerical increase in C-cell carcinomas were observed in males and females at all dose levels (>3 times human exposure).

In a 2-year carcinogenicity study in Sprague Dawley rats, subcutaneous doses of 0.0025, 0.01, 0.025 and 0.1 mg/kg/day were administered (below quantification, 0.8-, 1.8- and 11-fold the exposure at the MRHD). A statistically significant increase in thyroid C-cell adenomas was observed in males and females at all dose levels, and a statistically significant increase in thyroid C-cell carcinomas was observed in males at ≥0.01 mg/kg/day, at clinically relevant exposures.

Human relevance of thyroid C-cell tumors in rats is unknown and could not be determined by clinical studies or nonclinical studies [see Boxed Warning, Warnings and Precautions (5.1)].

Semaglutide was not mutagenic or clastogenic in a standard battery of genotoxicity tests (bacterial mutagenicity (Ames), human lymphocyte chromosome aberration, rat bone marrow micronucleus).

In a combined fertility and embryo-fetal development study in rats, subcutaneous doses of 0.01, 0.03 and 0.09 mg/kg/day (0.2-, 0.7- and 2.1-fold the MRHD) were administered to male and female rats. Males were dosed for 4 weeks prior to mating, and females were dosed for 2 weeks prior to mating and throughout organogenesis until Gestation Day 17. No effects were observed on male fertility. In females, an increase in estrus cycle length was observed at all dose levels, together with a small reduction in numbers of corpora lutea at ≥0.03 mg/kg/day. These effects were likely an adaptive response secondary to the pharmacological effect of semaglutide on food consumption and body weight.

13.2 Animal Toxicology and/or Pharmacology

RYBELSUS and OZEMPIC tablets contain SNAC as an absorption enhancer. Increase in lactate levels and decrease in glucose levels in the plasma and cerebrospinal fluid (CSF) were observed in mechanistic studies with SNAC in rats. Small but statistically significant increases in lactate levels (up to 2-fold) were observed in a few animals at approximately the clinical exposure. At higher exposures these findings were associated with moderate to marked adverse clinical signs (lethargy, abnormal respiration, ataxia, reduced activity, body tone and reflexes) and marked decreases in plasma and CSF glucose levels. These findings are consistent with inhibition of cellular respiration and lead to mortality at SNAC concentrations ≥100-times the clinical Cmax.

14 CLINICAL STUDIES

14.1 Overview of Clinical Studies

The effectiveness of OZEMPIC tablets (1.5 mg, 4 mg and 9 mg strengths) [see Dosage and Administration (2.2)] and RYBELSUS (3 mg, 7, mg and 14 mg strengths) [see Dosage and Administration (2.3)] has been established as an adjunct to diet and exercise to improve glycemic control in adults with type 2 diabetes mellitus based on adequate and well-controlled studies of RYBELSUS in adult patients with type 2 diabetes mellitus [see Clinical Pharmacology (12.3)]. Below is a display of the efficacy results of the adequate and well-controlled studies of RYBELSUS, referred to below as semaglutide tablets, in adult patients with type 2 diabetes mellitus.

Semaglutide tablets have been studied as monotherapy and in combination with metformin, sulfonylureas, sodium-glucose co-transporter-2 (SGLT-2) inhibitors, insulins, and thiazolidinediones in patients with type 2 diabetes mellitus. The efficacy of semaglutide tablets was compared with placebo, empagliflozin, sitagliptin and liraglutide. Semaglutide tablets have also been studied in patients with type 2 diabetes mellitus with mild and moderate renal impairment.

In patients with type 2 diabetes mellitus, semaglutide tablets produced clinically significant reduction from baseline in HbA1c compared with placebo.

The efficacy of semaglutide tablets was not impacted by baseline age, sex, race, ethnicity, BMI, body weight, duration of diabetes and degree of renal impairment.

14.2 Monotherapy Use of Semaglutide Tablets in Patients with Type 2 Diabetes Mellitus

In a 26-week double-blind trial (Trial 1, NCT02906930), 703 adult patients with type 2 diabetes mellitus inadequately controlled with diet and exercise were randomized to semaglutide tablets 3 mg, semaglutide tablets 7 mg or semaglutide tablets14 mg orally once daily or placebo. Patients had a mean age of 55 years and 51% were men. The mean duration of type 2 diabetes mellitus was 3.5 years, and the mean BMI was 32 kg/m^2. Overall, 75% were White, 5% were Black or African American and 17% were Asian; 26% identified as Hispanic or Latino ethnicity.

Monotherapy with semaglutide tablets7 mg and semaglutide tablets 14 mg tablets once daily for 26 weeks resulted in a statistically significant reduction in HbA1c compared with placebo (see Table 4).

Table 4. Trial 1 Results at Week 26 in a Monotherapy Trial of Semaglutide Tablets in Adult Patients with Type 2 Diabetes Mellitus Inadequately Controlled with Diet and Exercise

 | Placebo | Semaglutide Tablets; 7 mg | Semaglutide Tablets; 14 mg
Intent-to-Treat (ITT) Population (N)a | 178 | 175 | 175
HbA1c (%)
Baseline (mean) | 7.9 | 8 | 8
Change at Week 26b | -0.3 | -1.2 | -1.4
Difference from placebob [95% CI] |  | -0.9; [-1.1; -0.6]c | -1.1; [-1.3; -0.9]c
Patients (%) achieving HbA1c <7% | 31 | 69 | 77
FPG (mg/dL)
Baseline (mean) | 160 | 162 | 158
Change at Week 26b | -3 | -28 | -33

a The intent-to-treat population includes all randomized patients. At Week 26, the primary HbA1c endpoint was missing for 5.6%, 8.6% and 8.6% of patients randomized to placebo, semaglutide tablets 7 mg and semaglutide tablets14 mg, respectively. Missing data were imputed by a pattern mixture model using multiple imputation (MI). Pattern was defined by randomized treatment and treatment status at Week 26. During the trial, additional anti-diabetic medication was initiated as an add on to randomized treatment by 15%, 2% and 1% of patients randomized to placebo, semaglutide tablets 7 mg and semaglutide tablets 14 mg, respectively.

b Estimated using an ANCOVA model based on data irrespectively of discontinuation of trial product or initiation of rescue medication adjusted for baseline value and region.

c p<0.001 (unadjusted 2-sided) for superiority, controlled for multiplicity.

The mean baseline body weight was 88.6 kg, 89 kg and 88.1 kg in the placebo, semaglutide tablets 7 mg, and semaglutide tablets 14 mg arms, respectively. The mean changes from baseline to week 26 were -1.4 kg, -2.3 kg and -3.7 kg in the placebo, semaglutide tablets7 mg and semaglutide tablets 14 mg arms, respectively. The difference from placebo (95% CI) for semaglutide tablets 7 mg was -0.9 kg (-1.9, 0.1) and for semaglutide tablets 14 mg was -2.3 kg (-3.1, -1.5).

14.3 Combination Therapy Use of Semaglutide Tablets in Patients with Type 2 Diabetes Mellitus

Combination with Metformin

In a 26-week trial (Trial 2, NCT02863328), 822 adult patients with type 2 mellitus diabetes were randomized to semaglutide tablets 14 mg orally once daily or empagliflozin 25 mg orally once daily, all in combination with metformin. Patients had a mean age of 58 years and 50% were men. The mean duration of type 2 diabetes mellitus was 7.4 years and the mean BMI was 33 kg/m^2. Overall, 86% were White, 7% were Black or African American and 6% were Asian; 24% identified as Hispanic or Latino ethnicity.

Treatment with semaglutide tablets 14 mg once daily for 26 weeks resulted in a statistically significant reduction in HbA1c compared to empagliflozin 25 mg once daily (see Table 5).

Table 5. Trial 2 Results at Week 26 in a Trial of Semaglutide Tablets Compared to Empagliflozin in Adult Patients with Type 2 Diabetes Mellitus in Combination with Metformin

 | Semaglutide Tablets; 14 mg | Empagliflozin; 25 mg
Intent-to-Treat (ITT) Population (N)a | 411 | 410
HbA1c (%)
Baseline (mean) | 8.1 | 8.1
Change at Week 26b | -1.3 | -0.9
Difference from empagliflozinb [95% CI] | -0.4; [-0.6, -0.3]c
Patients (%) achieving HbA1c <7% | 67 | 40
FPG (mg/dL)
Baseline (mean) | 172 | 174
Change at Week 26b | -36 | -36

a The intent-to-treat population includes all randomized patients. At Week 26, the primary HbA1c endpoint was missing for 4.6% and 3.7% of patients randomized to semaglutide tablets 14 mg and empagliflozin 25 mg, respectively. Missing data were imputed by a pattern mixture model using multiple imputation (MI). Pattern was defined by randomized treatment and treatment status at Week 26. During the trial, additional anti-diabetic medication was initiated as an add on to randomized treatment by 1.9% and 1.2% of patients randomized to semaglutide tablets 14 mg and empagliflozin 25 mg, respectively.

b Estimated using an ANCOVA based on data irrespectively of discontinuation of trial product or initiation of rescue medication adjusted for baseline value and region.

c p<0.001 (unadjusted 2-sided) for superiority, controlled for multiplicity.

The mean baseline body weight was 91.9 kg and 91.3 kg in the semaglutide tablets 14 mg and empagliflozin 25 mg arms, respectively. The mean changes from baseline to Week 26 were -3.8 kg and -3.7 kg in the semaglutide tablets 14 mg and empagliflozin 25 mg arms, respectively. The difference from empagliflozin (95% CI) for semaglutide tablets 14 mg was -0.1 kg (-0.7, 0.5).

Combination with Metformin or Metformin with Sulfonylurea

In a 26-week, double-blind trial (Trial 3, NCT02607865), 1864 adult patients with type 2 mellitus diabetes on metformin alone or metformin with sulfonylurea were randomized to semaglutide tablets 3 mg, semaglutide tablets 7 mg, semaglutide tablets 14 mg orally once daily or sitagliptin 100 mg once daily. Patients had a mean age of 58 years and 53% were men. The mean duration of type 2 diabetes mellitus was 8.6 years, and the mean BMI was 32 kg/m^2. Overall, 71% were White, 9% were Black or African American and 13% were Asian; 17% identified as Hispanic or Latino ethnicity.

Treatment with semaglutide tablets 7 mg and semaglutide tablets 14 mg once daily for 26 weeks resulted in a statistically significant reduction in HbA1c compared to sitagliptin 100 mg once daily (see Table 6).

Table 6. Trial 3 Results at Week 26 in a Trial of Semaglutide Tablets Compared to Sitagliptin 100 mg Once Daily in Adult Patients with Type 2 Diabetes Mellitus in Combination with Metformin or Metformin with Sulfonylurea

 | Semaglutide Tablets; 7 mg | Semaglutide Tablets; 14 mg | Sitagliptin; 100 mg
Intent-to-Treat (ITT) Population (N)a | 465 | 465 | 467
HbA1c (%)
Baseline (mean) | 8.4 | 8.3 | 8.3
Change at Week 26b | -1 | -1.3 | -0.8
Difference from sitagliptinb [95% CI] | -0.3; [-0.4; -0.1]c | -0.5; [-0.6; -0.4]c
Patients (%) achieving HbA1c <7% | 44 | 56 | 32
FPG (mg/dL)
Baseline (mean) | 170 | 168 | 172
Change at Week 26b | -21 | -31 | -15

a The intent-to-treat population includes all randomized patients. At Week 26, the primary HbA1c endpoint was missing for 5.8%, 6.2% and 4.5% of patients randomized to semaglutide tablets 7 mg, semaglutide tablets 14 mg and sitagliptin 100 mg, respectively. Missing values were imputed by a pattern mixture model using multiple imputation (MI). Pattern was defined by randomized treatment and treatment status at Week 26. During the trial, additional anti-diabetic medication was initiated as an add on to randomized treatment by 2.4%, 1.1% and 2.8% of patients randomized to semaglutide tablets 7 mg, semaglutide tablets 14 mg and sitagliptin 100 mg, respectively.

b Estimated using an ANCOVA based on data irrespectively of discontinuation of trial product or initiation of rescue medication adjusted for baseline value, background medication and region.

c p<0.001 (unadjusted 2-sided) for superiority, controlled for multiplicity.

The mean baseline body weight was 91.3 kg, 91.2 kg and 90.9 kg in the semaglutide tablets 7 mg, semaglutide tablets 14 mg and sitagliptin 100 mg arms, respectively. The mean changes from baseline to Week 26 were -2.2 kg, -3.1 kg and -0.6 kg in the semaglutide tablets 7 mg, semaglutide tablets 14 mg and sitagliptin 100 mg arms, respectively. The difference from sitagliptin (95% CI) for semaglutide tablets 7 mg was -1.6 kg (-2.0, -1.1) and semaglutide tablets 14 mg was -2.5 kg (-3.0, -2.0).

Combination with Metformin or Metformin with SGLT-2 Inhibitors

In a 26-week, double-blind, double-dummy trial (Trial 4, NCT02863419), 711 adult patients with type 2 diabetes mellitus on metformin alone or metformin with SGLT-2 inhibitors were randomized to semaglutide tablets 14 mg orally once daily, liraglutide 1.8 mg subcutaneous injection once daily or placebo. Patients had a mean age of 56 years and 52% were men. The mean duration of type 2 diabetes mellitus was 7.6 years and the mean BMI was 33 kg/m^2. Overall, 73% were White, 4% were Black or African American and 13% were Asian; 6% identified as Hispanic or Latino ethnicity.

Treatment with semaglutide tablets 14 mg once daily for 26 weeks resulted in statistically significant reductions in HbA1c compared to placebo. Treatment with semaglutide tablets 14 mg once daily for 26 weeks resulted in non-inferior reductions in HbA1c compared to liraglutide 1.8 mg (see Table 7).

Table 7. Trial 4 Results at Week 26 in a Trial of Semaglutide Tablets Compared to Liraglutide and Placebo in Adult Patients with Type 2 Diabetes Mellitus in Combination with Metformin or Metformin with SGLT-2i

 | Placebo | Semaglutide Tablets; 14 mg | Liraglutide; 1.8 mg
Intent-to-Treat (ITT) Population (N)a | 142 | 285 | 284
HbA1c (%)
Baseline (mean) | 7.9 | 8 | 8
Change at Week 26b | -0.2 | -1.2 | -1.1
Difference from placebob [95% CI] |  | -1.1; [-1.2; -0.9]c
Difference from liraglutideb [95% CI] |  | -0.1; [-0.3; 0]
Patients (%) achieving HbA1c <7% | 14 | 68 | 62
FPG (mg/dL)
Baseline (mean) | 167 | 167 | 168
Change at Week 26b | -7 | -36 | -34

a The intent-to-treat population includes all randomized patients. At Week 26, the primary HbA1c endpoint was missing for 5.6%, 4.2% and 2.5% of patients randomized to placebo, liraglutide 1.8 mg and semaglutide tablets 14 mg, respectively. Missing values were imputed by a pattern mixture model using multiple imputation (MI). Pattern was defined by randomized treatment and treatment status at Week 26. During the trial, additional anti-diabetic medication was initiated as an add on to randomized treatment by 7.7%, 3.2% and 3.5% of patients randomized to placebo, liraglutide 1.8 mg and semaglutide tablets 14 mg respectively.

b Estimated using an ANCOVA based on data irrespectively of discontinuation of trial product or initiation of rescue medication adjusted for baseline value, background medication and region.

c p<0.001 (unadjusted 2-sided) for superiority, controlled for multiplicity.

The mean baseline body weight was 93.2 kg, 95.5 kg and 92.9 kg in the placebo, liraglutide 1.8 mg and semaglutide tablets 14 mg arms, respectively. The mean changes from baseline to Week 26 were -0.5 kg, -3.1 kg and -4.4 kg in the placebo, liraglutide 1.8 mg and semaglutide tablets 14 mg arms, respectively. The difference from placebo (95% CI) for semaglutide tablets 14 mg was -3.8 kg (-4.7, -3). The difference from liraglutide 1.8 mg for semaglutide tablets 14 mg was -1.2 (-1.9, -0.6).

Combination in patients with Type 2 Diabetes Mellitus and Moderate Renal Impairment with Metformin alone, Sulfonylurea alone, Basal Insulin alone or Metformin in Combination with either Sulfonylurea or Basal Insulin

In a 26-week, double-blind trial (Trial 5, NCT02827708), 324 adult patients with moderate renal impairment (eGFRCKD-EPI 30 to 59 mL/min/1.73 m^2) were randomized to semaglutide tablets 14 mg orally once daily or placebo once daily. Semaglutide tablets were added to the patient’s stable pre-trial antidiabetic regimen. The insulin dose was reduced by 20% at randomization for patients on basal insulin. Dose reduction of insulin and sulfonylurea was allowed in case of hypoglycemia; up titration of insulin was allowed but not beyond the pre-trial dose.

Patients had a mean age of 70 years and 48% were men. The mean duration of type 2 diabetes mellitus was 14 years and the mean BMI was 32 kg/m^2. Overall, 96% were White, 4% were Black or African American and 0.3% were Asian; 6.5% identified as Hispanic or Latino ethnicity. 39.5% of patients had an eGFR value of 30 to 44 mL/min/1.73 m^2.

Treatment with semaglutide tablets 14 mg once daily for 26 weeks resulted in a statistically significant reduction in HbA1c from baseline compared to placebo (see Table 8).

Table 8. Trial 5 Results at Week 26 in a Trial of Semaglutide Tablets Compared to Placebo in Patients with Moderate Renal Impairment

 | Placebo | Semaglutide Tablets; 14 mg
Intent-to-Treat (ITT) Population (N)a | 161 | 163
HbA1c (%)
Baseline (mean) | 7.9 | 8
Change at Week 26b | -0.2 | -1
Difference from placebob [95% CI] |  | -0.8; [-1.0; -0.6]c
Patients (%) achieving HbA1c <7% | 23 | 58
FPG (mg/dL)
Baseline (mean) | 164 | 164
Change at Week 26b | -7 | -28

a The intent-to-treat population includes all randomized patients including patients on rescue medication. At Week 26, the primary HbA1c endpoint was missing for 3.7% and 5.5% of patients randomized to placebo and semaglutide tablets 14 mg, respectively. Missing values were imputed by a pattern mixture model using multiple imputation (MI). Pattern was defined by randomized treatment and treatment status at Week 26. During the trial, additional anti-diabetic medication was initiated as an add on to randomized treatment by 10% and 4.3% of patients randomized to placebo and semaglutide tablets 14 mg, respectively.

b Estimated using an ANCOVA based on data irrespectively of discontinuation of trial product or initiation of rescue medication adjusted for baseline value, background medication, renal status and region.

c p<0.001 (unadjusted 2-sided) for superiority, controlled for multiplicity.

The mean baseline body weight was 90.4 kg and 91.3 kg in the placebo and semaglutide tablets 14 mg arms, respectively. The mean changes from baseline to Week 26 were -0.9 kg and -3.4 kg in the placebo and semaglutide tablets 14 mg arms, respectively. The difference from placebo (95% CI) for semaglutide tablets 14 mg was -2.5 kg (-3.2, -1.8).

Combination with Insulin with or without Metformin

In a 26-week double blind trial (Trial 6, NCT03021187), 731 adult patients with type 2 diabetes mellitus inadequately controlled on insulin (basal, basal/bolus or premixed) with or without metformin, were randomized to semaglutide tablets 3 mg, 7 mg and 14 mg orally once daily or placebo once daily. All patients reduced their insulin dose by 20% at randomization to reduce the risk of hypoglycemia. Patients were allowed to increase the insulin dose only up to the starting insulin dose prior to randomization.

Patients had a mean age of 61 years and 54% were men. The mean duration of type 2 diabetes mellitus was 15 years and the mean BMI was 31 kg/m^2. Overall, 51% were White, 7% were Black or African American and 36% were Asian; 13% identified as Hispanic or Latino ethnicity.

Treatment with semaglutide tablets 7 mg and 14 mg once daily for 26 weeks resulted in a statistically significant reduction in HbA1c from baseline compared to placebo once daily (see Table 9).

Table 9. Trial 6 Results at Week 26 in a Trial of Semaglutide Tablets Compared to Placebo in Adult Patients with Type 2 Diabetes Mellitus in Combination with Insulin alone or with Metformin

 | Placebo | Semaglutide Tablets; 7 mg | Semaglutide Tablets; 14 mg
Intent-to-Treat (ITT) Population (N)a | 184 | 182 | 181
HbA1c (%)
Baseline (mean) | 8.2 | 8.2 | 8.2
Change at Week 26b | -0.1 | -0.9 | -1.3
Difference from placebob [95% CI] |  | -0.9; [-1.1; -0.7]c | -1.2; [-1.4; -1]c
Patients (%) achieving HbA1c <7% | 7 | 43 | 58
FPG (mg/dL)
Baseline (mean) | 150 | 153 | 150
Change at Week 26b | 5 | -20 | -24

a The intent-to-treat population includes all randomized patients. At Week 26, the primary HbA1c endpoint was missing for 4.3%, 4.4% and 4.4% of patients randomized to placebo, semaglutide tablets 7 mg and semaglutide tablets 14 mg, respectively. Missing values were imputed by a pattern mixture model using multiple imputation (MI). Pattern was defined by randomized treatment and treatment status at Week 26. During the trial, additional anti-diabetic medication was initiated as an add on to randomized treatment by 4.9%, 1.1 % and 2.2% of patients randomized to placebo, semaglutide tablets 7 mg and semaglutide tablets 14 mg, respectively.

b Estimated using an ANCOVA based on data irrespectively of discontinuation of trial product or initiation of rescue medication adjusted for baseline value, background medication and region.

c p<0.001 (unadjusted 2-sided) for superiority, controlled for multiplicity.

The mean baseline body weight was 86 kg, 87.1 kg and 84.6 kg in the placebo, semaglutide tablets7 mg and semaglutide tablets 14 mg arms, respectively. The mean changes from baseline to Week 26 were -0.4 kg, -2.4 kg and -3.7 kg in the placebo, semaglutide tablets 7 mg and semaglutide tablets 14 mg arms, respectively. The difference from placebo (95% CI) for semaglutide tablets 7 mg was -2 kg (-3, -1) and for semaglutide tablets 14 mg was -3.3 kg (-4.2, -2.3).

14.4 Cardiovascular Outcomes Trial of Semaglutide Tablets in Adult Patients with Type 2 Diabetes Mellitus and High Risk of Having a Cardiovascular Event

Trial 7 (NCT03914326) was a randomized, double-blind, parallel-group, placebo-controlled trial. In this trial, 9,650 patients with type 2 diabetes mellitus and established cardiovascular (CV) disease and/or chronic kidney disease (CKD) (defined as eGFR <60 mL/min/1.73 m^2), were randomized to either once daily semaglutide tablets 14 mg or placebo, in addition to standard of care. The primary endpoint, major adverse cardiovascular events (MACE), was the time to first occurrence of a three-part composite outcome which included CV death, non-fatal myocardial infarction (MI) and non-fatal stroke.

Patients eligible to enter the trial were: 50 years of age or older and with established CV disease or CKD. In total, 5,468 patients (56.7%) had established CV disease without CKD, 1,241 (13%) had CKD only, and 2,620 (27%) had both CV disease and CKD. Most patients (97%) were treated with one or more glucose lowering medications at baseline: metformin (76%), insulin (51%), SGLT-2 inhibitor (27%), sulfonylurea (29%), and DPP-4 inhibitor (23%). At baseline, CV disease and risk factors were managed with lipid-lowering medications (89%), platelet-aggregation inhibitors including aspirin (77%), angiotensin converting enzyme inhibitors or angiotensin II receptor blockers (79%), and beta blockers (64%).

The mean age at baseline was 66.1 years, and 71% of the patients were men. Overall, 69% were White, 3% were Black or African American, and 23% were Asian; 14% identified as Hispanic or Latino ethnicity.

The mean duration of diabetes was 15.4 years, the mean BMI was 31.1 kg/m^2, the mean HbA1c was 8%, and the mean eGFR was 73.8 mL/min/1.73 m^2. Concomitant diseases included heart failure (23%), hypertension (91%), previous ischemic stroke (12%), previous MI (40%), and peripheral artery disease (16%). In total, 98.4% patients completed the trial, and the vital status was known at the end of the trial for 99.5%.

Semaglutide tablets significantly reduced the occurrence of MACE. The estimated hazard ratio for time to first MACE was 0.86 (95% CI: 0.77, 0.96) over the median follow-up duration of 49.6 months and 49.4 months for patients randomized to RYBELSUS and placebo, respectively. Refer to Table 10 and Figure 1. The treatment effect for the primary composite endpoint and its components in Trial 7 are shown in Table 10.

Table 10. Trial 7 Treatment Effect for MACE and its Components

 | Placebo; N=4,825 | Semaglutide Tablets 14 mg; N=4,825 | Hazard Ratio; vs Placebo; (95% CI)
Primary composite endpoint
MACE: Composite of CV death,; non-fatal MI, non-fatal stroke (time to first occurrence) | 668 (13.8%) | 579 (12%) | 0.86 (0.77, 0.96)
CV death | 320 (6.6%) | 301 (6.2%) | 0.93 (0.8, 1.09)
Non-fatal MI | 253 (5.2%) | 191 (4%) | 0.74 (0.61, 0.89)
Non-fatal stroke | 161 (3.3%) | 144 (3%) | 0.88 (0.7, 1.11)

Note: Data from the in-trial period based on full analysis set defined as all randomized patients.
Time from randomization to each endpoint was analyzed using a Cox proportional hazards model with treatment as categorical fixed factor. Subjects without events of interest were censored at the end of their in-trial period. For the primary endpoint the hazard ratio and CI were adjusted for the group sequential design using likelihood ratio ordering. CV death, non-fatal MI and non-fatal stroke are listed descriptively for supportive purpose. CV death includes both CV death and undetermined cause of death.
N=number of patients; %: percentage of participants in the full analysis set with at least one event; CI: confidence interval

Figure 1: Time to First Occurrence of a MACE in Trial 7

Data from the in-trial period based on full analysis set defined as all randomized patients. Cumulative incidence estimates are based on time from randomization to first EAC-confirmed MACE with non-CV death modeled as competing risk using the Aalen-Johansen estimator. Patients without events of interest were censored at the end of their in-trial observation period. Time from randomization to first MACE was analyzed using a Cox proportional hazards model with treatment as categorical fixed factor. The hazard ratio and confidence interval are adjusted for the group sequential design using the likelihood ratio ordering. HR: Hazard ratio; CI: confidence interval.

Cardiovascular Outcomes Trial in Patients with Type 2 Diabetes Mellitus and Cardiovascular Disease

Trial 8 (NCT02692716) was a multi-center, multi-national, placebo-controlled, double-blind trial. In this trial, 3,183 adult patients with inadequately controlled type 2 diabetes mellitus and atherosclerotic CV disease were randomized to semaglutide tablets 14 mg orally once daily or placebo for a median observation time of 16 months. The trial compared the risk of a MACE between semaglutide tablets 14 mg and placebo when added to current standard of care treatments for diabetes and cardiovascular CV disease. The primary endpoint, MACE, was the time to first occurrence of a three-part composite outcome which included cardiovascular death, non-fatal MI and non-fatal stroke.

Patients eligible to enter the trial were 50 years of age or older and had established, stable, CV, cerebrovascular, peripheral artery disease, CKD or NYHA class II and III heart failure or were 60 years of age or older and had other specified risk factors for CV disease. In total, 1,797 patients (56.5%) had established CV disease without CKD, 354 patients (11.1%) had CKD only, and 544 patients (17.1%) had both CV disease and CKD; 488 patients (15.3%) had CV risk factors without established CV disease or CKD. The mean age at baseline was 66 years and 68% were men. The mean duration of diabetes was 14.9 years and mean BMI was 32 kg/m^2. Overall, 72% were White, 6% were Black or African American and 20% were Asian; 16% identified as Hispanic or Latino ethnicity. Concomitant diseases of patients in this trial included, but were not limited to, heart failure (12%), history of ischemic stroke (8%) and history of a MI (36%). In total, 99.7% of the patients completed the trial and the vital status was known at the end of the trial for 100%.

For the primary analysis, a Cox proportional hazards model was used to test for non-inferiority of semaglutide tablets 14 mg to placebo for time to first MACE using a risk margin of 1.3. Type-1 error was controlled across multiple tests using a hierarchical testing strategy. Non‑inferiority to placebo was established, with a hazard ratio equal to 0.79 (95% CI: 0.57, 1.11) over the median observation time of 16-months. The proportion of patients who experienced at least one MACE was 3.8% (61/1591) for semaglutide tablets14 mg and 4.8% (76/1592) for placebo.

16 HOW SUPPLIED/STORAGE AND HANDLING

How Supplied

RYBELSUS strengths are available as follows:

Tablet Strength | Description | Package Configuration | NDC Number
3 mg | White to light yellow, oval shaped debossed with “3” on one side and “novo” on the other side | Bottle of 30 tablets | 0169-4303-30
7 mg | White to light yellow, oval shaped debossed with “7” on one side and “novo” on the other side | Bottle of 30 tablets | 0169-4307-30
14 mg | White to light yellow, oval shaped debossed with “14” on one side and “novo” on the other side | Bottle of 30 tablets | 0169-4314-30

OZEMPIC tablet strengths are available as follows:

Tablet Strength | Description | Package Configuration | NDC Number
1.5 mg | White to light yellow, round shaped debossed with “1.5” on one side and “novo” on the other side | Bottle of 30 tablets | 0169-1715-30
4 mg | White to light yellow, round shaped debossed with “4” on one side and “novo” on the other side | Bottle of 30 tablets | 0169-1704-30
9 mg | White to light yellow, round shaped debossed with “9” on one side and “novo” on the other side | Bottle of 30 tablets | 0169-1709-30

Storage and Handling

Store RYBELSUS and OZEMPIC tablets at 20°C to 25°C (68°F to 77°F); excursions permitted to 15°C to 30°C (59°F to 86°F) [see USP Controlled Room Temperature]. Store and dispense in the original bottle.

Store tablets in the original bottle until use to protect tablets from moisture. Store product in a dry place away from moisture.

17 PATIENT COUNSELING INFORMATION

Advise the patient to read the FDA-approved patient labeling (Medication Guide).

Risk of Thyroid C-cell Tumors

Inform patients that semaglutide causes thyroid C-cell tumors in rodents and that the human relevance of this finding has not been determined. Counsel patients to report symptoms of thyroid tumors (e.g., a lump in the neck, hoarseness, dysphagia or dyspnea) to their physician [see Boxed Warning, Warnings and Precautions (5.1)].

Acute Pancreatitis

Inform patients of the potential risk for acute pancreatitis and its symptoms: severe abdominal pain that may radiate to the back, and which may or may not be accompanied by nausea or vomiting. Instruct patients to discontinue RYBELSUS or OZEMPIC tablets promptly and contact their physician if pancreatitis is suspected [see Warnings and Precautions (5.2)].

Diabetic Retinopathy Complications

Inform patients to contact their physician if changes in vision are experienced during treatment with RYBELSUS or OZEMPIC tablets [see Warnings and Precautions (5.3)].

Hypoglycemia with Concomitant Use of Insulin Secretagogues or Insulin

Inform patients that the risk of hypoglycemia is increased when RYBELSUS or OZEMPIC tablets are used with an insulin secretagogue (such as a sulfonylurea) or insulin. Educate patients on the signs and symptoms of hypoglycemia [see Warnings and Precautions (5.4)].

Acute Kidney Injury Due to Volume Depletion

Inform patients of the potential risk of acute kidney injury due to dehydration associated with gastrointestinal adverse reactions. Advise patients to take precautions to avoid fluid depletion. Inform patients of the signs and symptoms of acute kidney injury and instruct them to promptly report any of these signs or symptoms or persistent (or extended) nausea, vomiting, and diarrhea to their healthcare provider [see Warnings and Precautions (5.5)].

Severe Gastrointestinal Adverse Reactions

Inform patients of the potential risk of severe gastrointestinal adverse reactions. Instruct patients to contact their healthcare provider if they have severe or persistent gastrointestinal symptoms [see Warnings and Precautions (5.6)].

Hypersensitivity Reactions

Inform patients that serious hypersensitivity reactions have been reported during postmarketing use of semaglutide tablets. Advise patients on the symptoms of hypersensitivity reactions and instruct them to stop taking RYBELSUS or OZEMPIC tablets and seek medical advice promptly if such symptoms occur [see Warnings and Precautions (5.7)].

Acute Gallbladder Disease

Inform patients of the potential risk for cholelithiasis or cholecystitis. Instruct patients to contact their physician if cholelithiasis or cholecystitis is suspected for appropriate clinical follow-up [see Warnings and Precautions (5.8)].

Pulmonary Aspiration During General Anesthesia or Deep Sedation:

Inform patients that RYBELSUS or OZEMPIC tablets may cause their stomach to empty more slowly which may lead to complications with anesthesia or deep sedation during planned surgeries or procedures. Instruct patients to inform healthcare providers prior to any planned surgeries or procedures if they are taking RYBELSUS or OZEMPIC tablets [see Warnings and Precautions (5.9)].

Pregnancy

Advise a pregnant woman of the potential risk to a fetus. Advise women to inform their healthcare provider if they are pregnant or intend to become pregnant [see Use in Specific Populations (8.1, 8.3)].

Lactation

RYBELSUS and OZEMPIC tablets pass into breast milk, and it is not known how it affects your baby. Advise females not to breastfeed during treatment with RYBELSUS or OZEMPIC tablets [see Use in Specific Populations (8.2)].

Females and Males of Reproductive Potential

Discontinue RYBELSUS or OZEMPIC tablets at least 2 months before a planned pregnancy due to the long washout period for semaglutide [see Use in Specific Populations (8.3)].

Marketed by:

Novo Nordisk Inc.

Plainsboro, NJ 08536

For additional information about RYBELSUS and OZEMPIC tablets contact:

Novo Nordisk Inc.

800 Scudders Mill Road

Plainsboro, NJ 08536

1-833-457-7455

RYBELSUS® and OZEMPIC® are registered trademarks of Novo Nordisk A/S.

Patent Information: http://www.novonordisk-us.com/products/product-patents.html

© 2026 Novo Nordisk

Medication Guide

RYBELSUS® (reb-EL-sus)

(semaglutide)

tablets, for oral use

OZEMPIC® (oh-ZEM-pick)

(semaglutide)

tablets, for oral use

Read this Medication Guide before you start using RYBELSUS or OZEMPIC tablets and each time you get a refill. There may be new information. This information does not take the place of talking to your healthcare provider about your medical condition or your treatment.

What is the most important information I should know about RYBELSUS and OZEMPIC tablets?

RYBELSUS and OZEMPIC tablets may cause serious side effects, including:

- Possible thyroid tumors, including cancer. Tell your healthcare provider if you get a lump or swelling in your neck, hoarseness, trouble swallowing, or shortness of breath. These may be symptoms of thyroid cancer. In studies with rodents, RYBELSUS and OZEMPIC tablets and other medicines that work like RYBELSUS and OZEMPIC tablets caused thyroid tumors, including thyroid cancer. It is not known if RYBELSUS and OZEMPIC tablets will cause thyroid tumors or a type of thyroid cancer called medullary thyroid carcinoma (MTC) in people.
- Do not use RYBELSUS or OZEMPIC tablets if you or any of your family have ever had a type of thyroid cancer called medullary thyroid carcinoma (MTC), or if you have an endocrine system condition called Multiple Endocrine Neoplasia syndrome type 2 (MEN 2).

What are RYBELSUS and OZEMPIC tablets?

RYBELSUS and OZEMPIC tablets are prescription medicines used:

- along with diet and exercise to improve blood sugar (glucose) in adults with type 2 diabetes mellitus.
- to reduce the risk of major cardiovascular events such as heart attack, stroke or death in adults with type 2 diabetes mellitus who are at high risk for these events.

It is not known if RYBELSUS and OZEMPIC tablets are safe and effective for use in children.

Do not use RYBELSUS or OZEMPIC tablets if:

- you or any of your family have ever had a type of thyroid cancer called medullary thyroid carcinoma (MTC) or if you have an endocrine system condition called Multiple Endocrine Neoplasia syndrome type 2 (MEN 2).
- you have had a serious allergic reaction to semaglutide or any of the ingredients in RYBELSUS or OZEMPIC tablets. See the end of this Medication Guide for a complete list of ingredients in RYBELSUS and OZEMPIC tablets.See “What are the possible side effects of RYBELSUS and OZEMPIC tablets?” for symptoms of a serious allergic reaction.

Before using RYBELSUS or OZEMPIC tablets, tell your healthcare provider if you have any other medical conditions, including if you:

- have or have had problems with your pancreas or kidneys.
- have a history of vision problems related to your diabetes.
- are scheduled to have surgery or other procedures that use anesthesia or deep sleepiness (deep sedation).
- are pregnant or plan to become pregnant. It is not known if RYBELSUS and OZEMPIC tablets will harm your unborn baby. You should stop using RYBELSUS or OZEMPIC tablets 2 months before you plan to become pregnant. Talk to your healthcare provider about the best way to control your blood sugar if you plan to become pregnant or while you are pregnant.
- are breastfeeding or plan to breastfeed. Breastfeeding is not recommended during treatment with RYBELSUS or OZEMPIC tablets.

Tell your healthcare provider about all the medicines you take,including prescription and over-the-counter medicines, vitamins, and herbal supplements. RYBELSUS and OZEMPIC tablets may affect the way some medicines work, and some medicines may affect the way RYBELSUS and OZEMPIC tablets work.

Before using RYBELSUS or OZEMPIC tablets, talk to your healthcare provider about low blood sugar and how to manage it. Tell your healthcare provider if you are taking other medicines to treat diabetes, including insulin or sulfonylureas.

Know the medicines you take. Keep a list of them to show your healthcare provider and pharmacist when you get a new medicine.

How should I take RYBELSUS or OZEMPIC tablets?

- Take RYBELSUS or OZEMPIC tablets exactly as your healthcare provider tells you to.
- Take 1 RYBELSUS or OZEMPIC tablet by mouth on an empty stomach in the morning with water (no more than 4 ounces). Do not take RYBELSUS or OZEMPIC tablets with any other liquids besides water.
- Do not split, crush, chew, or dissolve RYBELSUS or OZEMPIC tablets. Swallow RYBELSUS or OZEMPIC tablets whole.
- After 30 minutes, you can eat, drink, or take other oral medicines.
- Do not take more than 1 RYBELSUS or OZEMPIC tablet each day.
- If you miss a dose of RYBELSUS or OZEMPIC tablets, skip the missed dose and go back to your regular schedule.
- If you take too much RYBELSUS or OZEMPIC tablets, call your healthcare provider or Poison Help line at 1-800-222-1222, or go to the nearest hospital emergency room right away. Advice is also available online at poisonhelp.org.

Your dose of RYBELSUS or OZEMPIC tablets and other diabetes medicines may need to change because of:

change in level of physical activity or exercise, weight gain or loss, increased stress, illness, change in diet, fever, trauma, infection, surgery or because of other medicines you take.

What are the possible side effects of RYBELSUS and OZEMPIC tablets?

RYBELSUS and OZEMPIC tablets may cause serious side effects, including:

- See “What is the most important information I should know about RYBELSUS and OZEMPIC tablets?”
- inflammation of your pancreas (pancreatitis). Stop using RYBELSUS or OZEMPIC tablets and call your healthcare provider right away if you have severe pain in your stomach area (abdomen) that will not go away, with or without nausea or vomiting. Sometimes you may feel the pain from your abdomen to your back.
- changes in vision. Tell your healthcare provider if you have changes in vision during treatment with RYBELSUS or OZEMPIC tablets.
- low blood sugar (hypoglycemia). Your risk for getting low blood sugar may be higher if you use RYBELSUS or OZEMPIC tablets with another medicine that can cause low blood sugar, such as a sulfonylurea or insulin. Signs and symptoms of low blood sugar may include:

- dizziness or light-headedness

- blurred vision

- anxiety, irritability, or mood changes

- sweating

- slurred speech

- hunger

- confusion or drowsiness

- shakiness

- weakness

- headache

- fast heartbeat

- feeling jittery

- dehydration leading to kidney problems. Diarrhea, nausea, and vomiting may cause a loss of fluids (dehydration) which may cause kidney problems. It is important for you to drink fluids to help reduce your chance of dehydration. Tell your healthcare provider right away if you have nausea, vomiting, or diarrhea that does not go away.
- severe stomach problems. Stomach problems, sometimes severe, have been reported in people who use RYBELSUS or OZEMPIC tablets. Tell your healthcare provider if you have stomach problems that are severe or will not go away.
- serious allergic reactions. Stop using RYBELSUS or OZEMPIC tablets and get medical help right away, if you have any symptoms of a serious allergic reaction including:
- swelling of your face, lips, tongue or throat
- problems breathing or swallowing
- severe rash or itching
- fainting or feeling dizzy
- very rapid heartbeat
- gallbladder problems. Gallbladder problems have happened in some people who take RYBELSUS andOZEMPIC tablets. Tell your healthcare provider right away if you get symptoms of gallbladder problems, which may include:

- pain in your upper stomach (abdomen)

- yellowing of skin or eyes (jaundice)

- fever

- clay-colored stools

- food or liquid getting into the lungs during surgery or other procedures that use anesthesia or deep sleepiness (deep sedation). RYBELSUS and OZEMPIC tablets may increase the chance of food getting into your lungs during surgery or other procedures. Tell all your healthcare providers that you are taking RYBELSUS or OZEMPIC tablets before you are scheduled to have surgery or other procedures.

The most common side effects of RYBELSUS and OZEMPIC tablets may include nausea, stomach (abdominal) pain, diarrhea, decreased appetite, vomiting and constipation. Nausea, vomiting and diarrhea are most common when you first start RYBELSUS or OZEMPIC tablets.

Talk to your healthcare provider about any side effect that bothers you or does not go away. These are not all the possible side effects of RYBELSUS and OZEMPIC tablets.

Call your doctor for medical advice about side effects. You may report side effects to FDA at 1‑800‑FDA‑1088.

How should I store RYBELSUS and OZEMPIC tablets?

- Store RYBELSUS or OZEMPIC tablets at room temperature between 68°F and 77°F (20°C to 25°C).
- Store in a dry place away from moisture.
- Store tablets in the original closed RYBELSUS or OZEMPIC bottle until you are ready to take one. Do not store in any other container.
- Keep RYBELSUS, OZEMPIC tablets and all medicines out of the reach of children.

General information about the safe and effective use of RYBELSUS and OZEMPIC tablets.

Medicines are sometimes prescribed for purposes other than those listed in a Medication Guide. Do not use RYBELSUS or OZEMPIC tablets for a condition for which it was not prescribed. Do not give RYBELSUS or OZEMPIC tablets to other people, even if they have the same symptoms that you have. It may harm them. You can ask your pharmacist or healthcare provider for information about RYBELSUS or OZEMPIC tablets that is written for health professionals.

What are the ingredients in RYBELSUS and OZEMPIC tablets?

Active Ingredient in RYBELSUS and OZEMPIC: semaglutide

Inactive Ingredients in RYBELSUS: magnesium stearate, microcrystalline cellulose, povidone and salcaprozate sodium

Inactive ingredients in OZEMPIC: magnesium stearate and salcaprozate sodium

Marketed by: Novo Nordisk Inc., Plainsboro, NJ 08536

RYBELSUS® and OZEMPIC® are registered trademarks of Novo Nordisk A/S.

Patent Information: http://www.novonordisk-us.com/products/product-patents.html

© 2026 Novo Nordisk

For more information, go to www.RYBELSUS.com, www.OZEMPIC.com or call 1-833-GLP-PILL.

This Medication Guide has been approved by the U.S. Food and Drug Administration. Revised: 1/2026

PACKAGE/LABEL PRINCIPAL DISPLAY PANEL – OZEMPIC 1.5 mg tablets

NDC 0169-1715-30List 171530
OZEMPIC® 1.5 mg

(semaglutide) Tablets

1.5 mg

Rx only

DISPENSE WITH MEDICATION GUIDE

Note to Pharmacist: Individual strengths of semaglutide are not substitutable on a mg-to-mg basis

New Formulation of semaglutide

30 tablets

PACKAGE/LABEL PRINCIPAL DISPLAY PANEL – OZEMPIC 4 mg tablets

NDC 0169-1704-30List 170430
OZEMPIC® 4 mg

(semaglutide) Tablets

4 mg

Rx only

DISPENSE WITH MEDICATION GUIDE

Note to Pharmacist: Individual strengths of semaglutide are not substitutable on a mg-to-mg basis

New Formulation of semaglutide

30 tablets

PACKAGE/LABEL PRINCIPAL DISPLAY PANEL – OZEMPIC 9 mg tablets

NDC 0169-1709-30List 170930
OZEMPIC® 9 mg

(semaglutide) Tablets

9 mg

Rx only

DISPENSE WITH MEDICATION GUIDE

Note to Pharmacist: Individual strengths of semaglutide are not substitutable on a mg-to-mg basis

New Formulation of semaglutide

30 tablets

PACKAGE/LABEL PRINCIPAL DISPLAY PANEL – RYBELSUS 3 mg bottle

NDC 0169-4303-30List 430330
RYBELSUS® 3 mg

(semaglutide) Tablets

3 mg

Once daily

Oral use only

Rx only

DISPENSE WITH MEDICATION GUIDE

30 tablets

PACKAGE/LABEL PRINCIPAL DISPLAY PANEL – RYBELSUS 7 mg bottle

NDC 0169-4307-30List 430730
RYBELSUS® 7 mg

(semaglutide) Tablets

7 mg

Once daily

Oral use only

Rx only

DISPENSE WITH MEDICATION GUIDE

30 tablets

PACKAGE/LABEL PRINCIPAL DISPLAY PANEL – RYBELSUS 14 mg bottle

NDC 0169-4314-30List 431430
RYBELSUS® 14 mg

(semaglutide) Tablets

14 mg

Once daily

Oral use only

Rx only

DISPENSE WITH MEDICATION GUIDE

30 tablets

PACKAGE/LABEL PRINCIPAL DISPLAY PANEL – RYBELSUS 3 mg blister

NDC 0169-4303-13List 430313
RYBELSUS®3 mg

(semaglutide) Tablets

3 mg

Once daily

Each tablet contains 3 mg semaglutide

Oral use only

Rx only

Dispense the Enclosed Medication Guide to Each Patient

30 tablets

3 blister packs. Each pack contains 10 tablets.

Open Here

PACKAGE/LABEL PRINCIPAL DISPLAY PANEL – RYBELSUS 7 mg blister

NDC 0169-4307-13List 430713
RYBELSUS®7 mg

(semaglutide) Tablets

7 mg

Once daily

Each tablet contains 7 mg semaglutide

Oral use only

Rx only

Dispense the Enclosed Medication Guide to Each Patient

30 tablets

3 blister packs. Each pack contains 10 tablets.

Open Here

PACKAGE/LABEL PRINCIPAL DISPLAY PANEL – RYBELSUS 14 mg blister

NDC 0169-4314-13List 431413
RYBELSUS®14 mg

(semaglutide) Tablets

14 mg

Once daily

Each tablet contains 14 mg semaglutide

Oral use only

Rx only

Dispense the Enclosed Medication Guide to Each Patient

30 tablets

3 blister packs. Each pack contains 10 tablets.

Open Here

PACKAGE/LABEL PRINCIPAL DISPLAY PANEL – R2 1.5 mg bottle

NDC 0169-4815-30List 481530
RYBELSUS® 1.5 mg

(semaglutide) Tablets

1.5 mg

Rx only

DISPENSE WITH MEDICATION GUIDE

Note to Pharmacist: Individual strengths of Rybelsus are not substitutable on a mg-to-mg basis

New Formulation (Formulation R2)

30 tablets

PACKAGE/LABEL PRINCIPAL DISPLAY PANEL – R2 4 mg bottle

NDC 0169-4804-30List 480430
RYBELSUS® 4 mg

(semaglutide) Tablets

4 mg

Rx only

DISPENSE WITH MEDICATION GUIDE

Note to Pharmacist: Individual strengths of Rybelsus are not substitutable on a mg-to-mg basis

New Formulation (Formulation R2)

30 tablets

PACKAGE/LABEL PRINCIPAL DISPLAY PANEL – R2 9 mg bottle

NDC 0169-4809-30List 480930
RYBELSUS® 9 mg

(semaglutide) Tablets

9 mg

Rx only

DISPENSE WITH MEDICATION GUIDE

Note to Pharmacist: Individual strengths of Rybelsus are not substitutable on a mg-to-mg basis

New Formulation (Formulation R2)

30 tablets